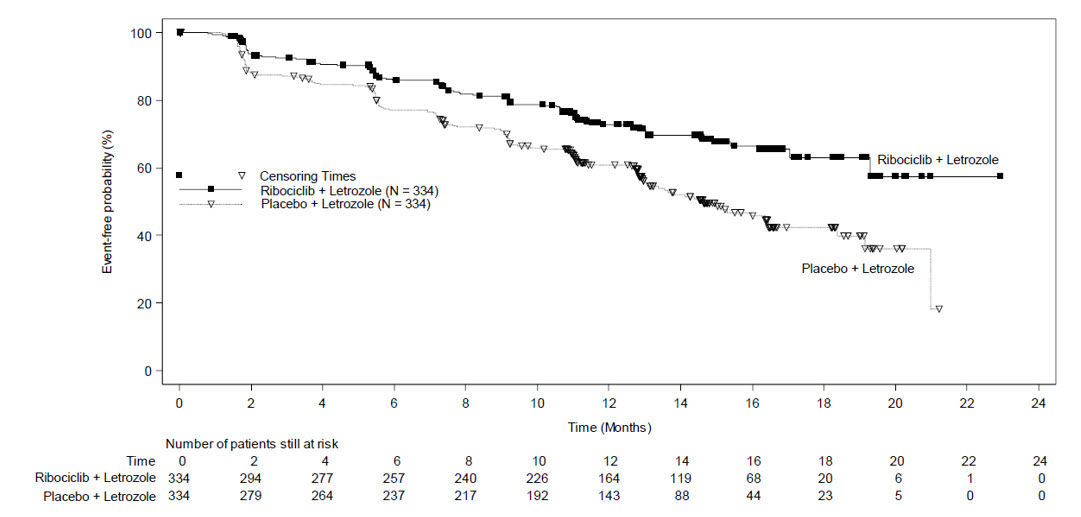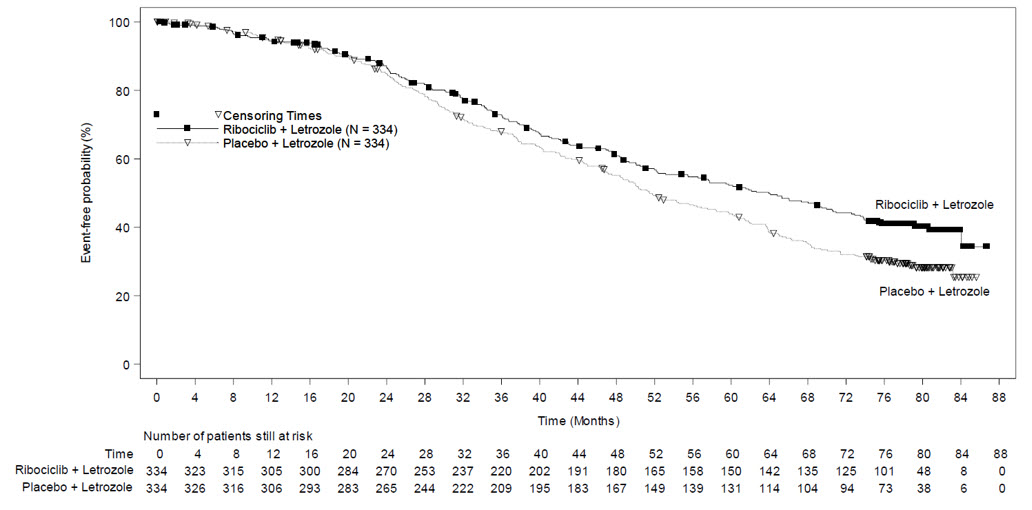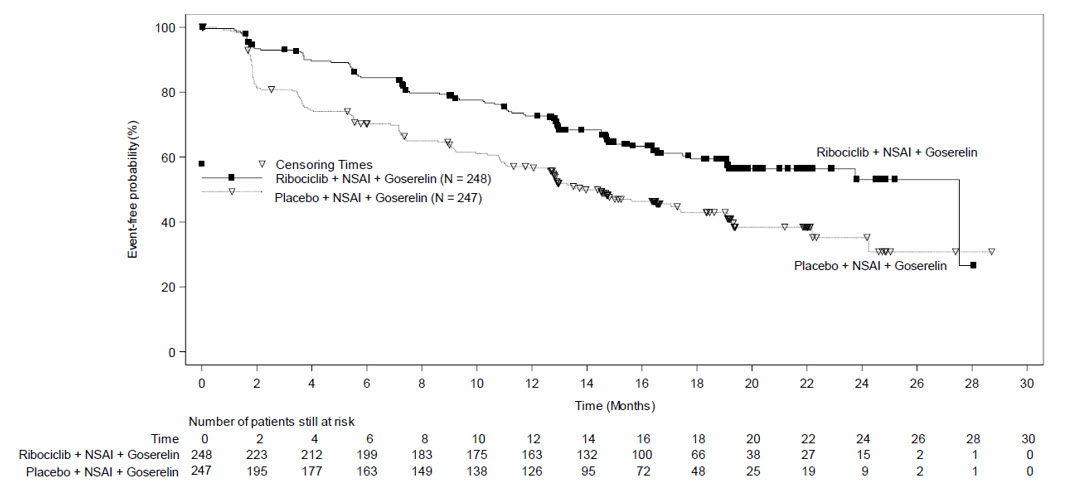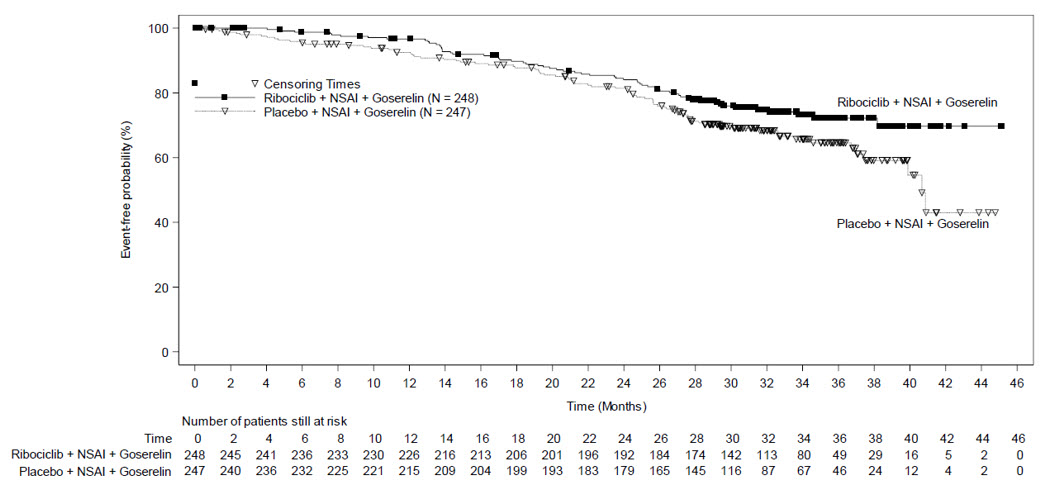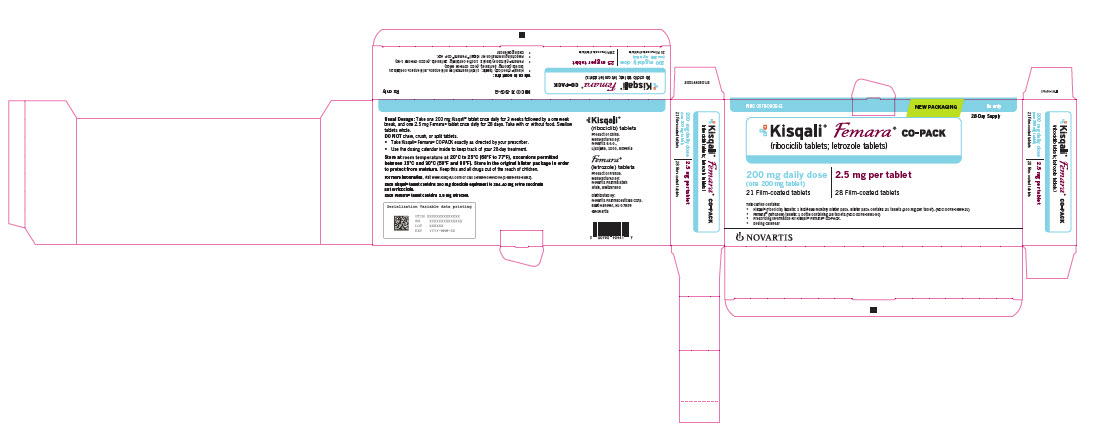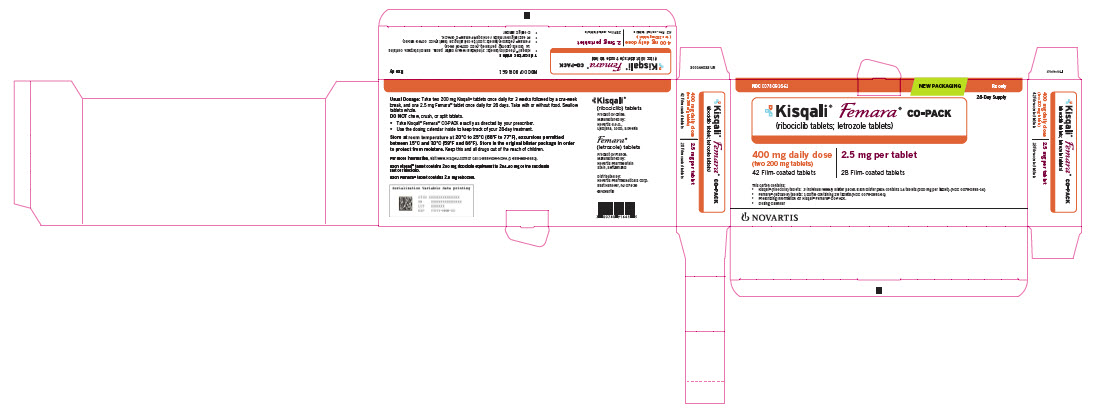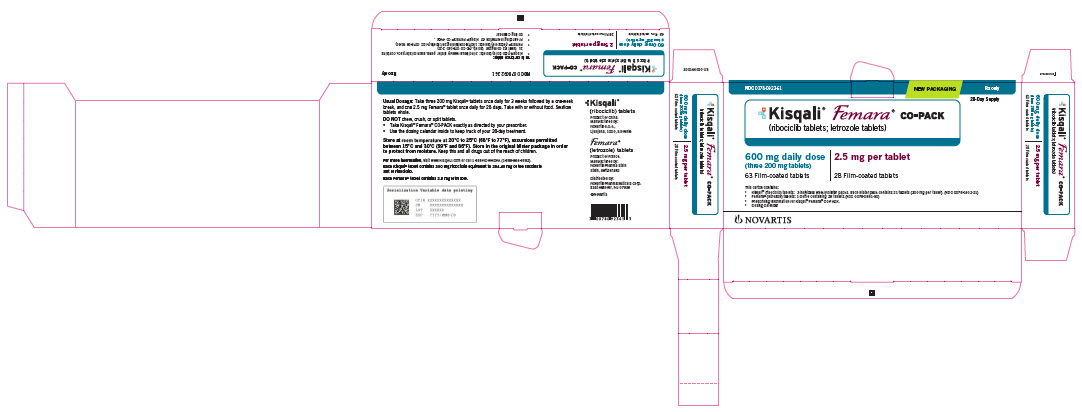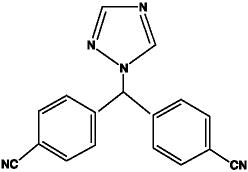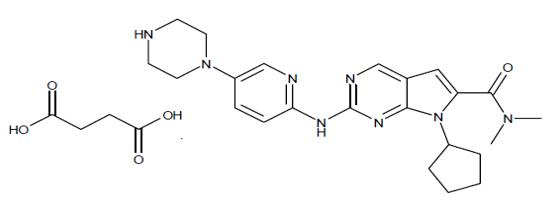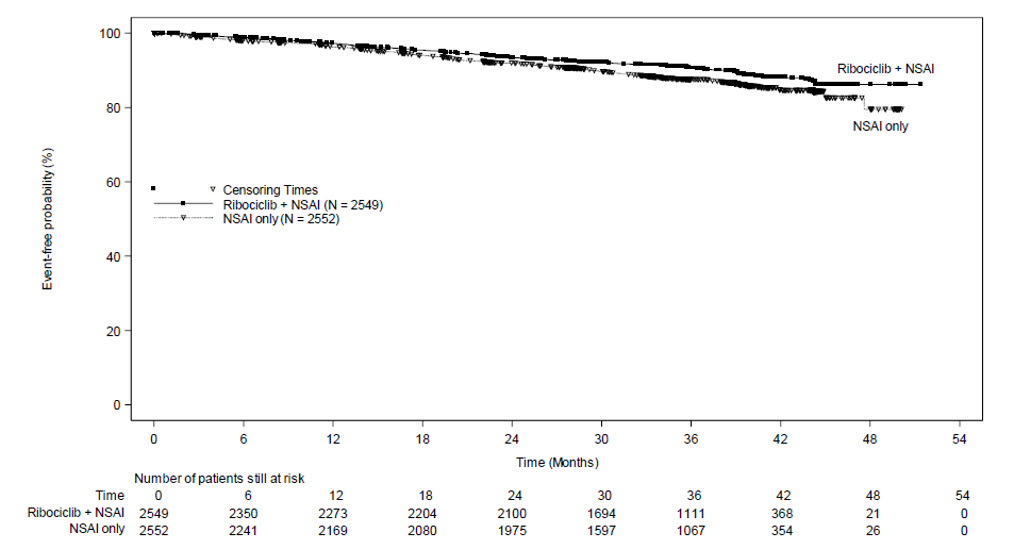 DRUG LABEL: KISQALI FEMARA CO-PACK
NDC: 0078-0909 | Form: KIT | Route: ORAL
Manufacturer: Novartis Pharmaceuticals Corporation
Category: prescription | Type: HUMAN PRESCRIPTION DRUG LABEL
Date: 20250916

ACTIVE INGREDIENTS: LETROZOLE 2.5 mg/1 1; RIBOCICLIB SUCCINATE 200 mg/1 1
INACTIVE INGREDIENTS: SILICON DIOXIDE; FERRIC OXIDE RED; HYPROMELLOSES; LACTOSE MONOHYDRATE; MAGNESIUM STEARATE; STARCH, CORN; CELLULOSE, MICROCRYSTALLINE; POLYETHYLENE GLYCOL; SODIUM STARCH GLYCOLATE TYPE A POTATO; TALC; TITANIUM DIOXIDE; SILICON DIOXIDE; CROSPOVIDONE; HYDROXYPROPYL CELLULOSE, UNSPECIFIED; MAGNESIUM STEARATE; MICROCRYSTALLINE CELLULOSE; FERROSOFERRIC OXIDE; FERRIC OXIDE RED; LECITHIN, SOYBEAN; POLYVINYL ALCOHOL, UNSPECIFIED; TALC; TITANIUM DIOXIDE; XANTHAN GUM

HIGHLIGHTS OF PRESCRIBING INFORMATION

These highlights do not include all the information needed to use KISQALI FEMARA CO-PACK safely and effectively. See full prescribing information for KISQALI FEMARA CO-PACK.
KISQALI® FEMARA® CO-PACK (ribociclib tablets; letrozole tablets), co-packaged for oral use
Initial U.S. Approval: 2017

RECENT MAJOR CHANGES

Indications and Usage (1.1) | 9/2024
Dosage and Administration (2.1, 2.2) | 9/2024
Warnings and Precautions (5.1, 5.3, 5.4, 5.5) | 9/2024

1 INDICATIONS AND USAGE

KISQALI FEMARA CO-PACK, a co-packaged product containing ribociclib, a kinase inhibitor, and letrozole, an aromatase inhibitor, is indicated:

- for the adjuvant treatment of adults with hormone receptor (HR)-positive, human epidermal growth factor receptor 2 (HER2)-negative stage II and III early breast cancer at high risk of recurrence. (1)
- as initial endocrine-based therapy for the treatment of adults with HR-positive, HER2-negative advanced or metastatic breast cancer therapy. (1)

2 DOSAGE AND ADMINISTRATION

KISQALI FEMARA CO-PACK tablets are taken in combination orally with or without food. (2)

Early Breast Cancer

- KISQALI recommended starting dose: 400 mg orally (two 200 mg tablets) taken once daily for 21 consecutive days followed by 7 days off KISQALI treatment. (2.1)

Advanced or Metastatic Breast Cancer

- KISQALI recommended starting dose: 600 mg orally (three 200 mg tablets) taken once daily for 21 consecutive days followed by 7 days off KISQALI treatment. (2.1)

KISQALI dose interruption, reduction, and/or discontinuation may be required based on individual safety and tolerability. (2.2)
FEMARA: 2.5 mg (one tablet) continuously for a 28-day cycle. (2.1)

3 DOSAGE FORMS AND STRENGTHS

Tablets:

- KISQALI: 200 mg (3)
- FEMARA: 2.5 mg (3)

4 CONTRAINDICATIONS

Known hypersensitivity to letrozole, or to any excipients of FEMARA. (4)

5 WARNINGS AND PRECAUTIONS

- Interstitial Lung Disease (ILD)/Pneumonitis: Patients treated with CDK 4/6 inhibitors should be monitored for pulmonary symptoms indicative of ILD/pneumonitis. Interrupt and evaluate patients with new or worsening respiratory symptoms suspected to be due to ILD/pneumonitis. Permanently discontinue KISQALI in patients with recurrent symptomatic or severe ILD/pneumonitis. (2.2, 5.1)
- Severe Cutaneous Adverse Reactions (SCARs): Stevens-Johnson syndrome (SJS), toxic epidermal necrolysis (TEN), and drug reaction with eosinophilia and systemic symptoms (DRESS) can occur with KISQALI treatment. Permanently discontinue KISQALI in patients with SCARs or other life-threatening cutaneous reactions. (2.2, 5.2)
- QT Interval Prolongation: Monitor electrocardiograms (ECGs) and electrolytes prior to initiation of treatment with KISQALI. Repeat ECGs at approximately Day 14 of the first cycle, and as clinically indicated. Monitor electrolytes at the beginning of each cycle for 6 cycles, and as clinically indicated. Avoid using KISQALI with drugs known to prolong QT interval and/or strong CYP3A inhibitors. (2.2, 5.3, 7.1, 7.4)
- Hepatobiliary Toxicity: Increases in serum transaminase and bilirubin levels have been observed. Perform liver function tests (LFTs) before initiating treatment with KISQALI FEMARA CO-PACK. Monitor LFTs every 2 weeks for the first 2 cycles, at the beginning of each subsequent 4 cycles, and as clinically indicated. (2.2, 5.4)
- Neutropenia: Perform complete blood count (CBC) before initiating therapy with KISQALI FEMARA CO-PACK. Monitor CBC every 2 weeks for the first 2 cycles, at the beginning of each subsequent 4 cycles, and as clinically indicated. (2.2, 5.5)
- Embryo-Fetal Toxicity: Can cause fetal harm when administered to pregnant women. Advise females of reproductive potential of the potential risk to a fetus and to use effective contraception during therapy. (5.6, 8.1, 8.3)

6 ADVERSE REACTIONS

- In patients with early breast cancer, the most common (incidence ≥ 20%) adverse reactions, including laboratory abnormalities, are lymphocytes decreased, leukocytes decreased, neutrophils decreased, hemoglobin decreased, alanine aminotransferase increased, aspartate aminotransferase increased, infections, creatinine increased, platelets decreased, headache, nausea, and fatigue. (6)
- In patients with advanced or metastatic breast cancer, the most common (incidence ≥ 20%) adverse reactions, including laboratory abnormalities, are leukocytes decreased, neutrophils decreased, hemoglobin decreased, lymphocytes decreased, alanine aminotransferase increased, aspartate aminotransferase increased, infections, nausea, fatigue, platelets decreased, diarrhea, headache, alopecia, vomiting, back pain, constipation, cough, rash, creatinine increased, and abdominal pain. (6)

To report SUSPECTED ADVERSE REACTIONS, contact Novartis Pharmaceuticals Corporation at 1-888-669-6682 or FDA at 1-800-FDA-1088 or www.fda.gov/medwatch.

7 DRUG INTERACTIONS

- CYP3A4 Inhibitors: Avoid concomitant use of KISQALI FEMARA CO-PACK with strong CYP3A inhibitors. If strong inhibitors cannot be avoided, reduce KISQALI dose. (2.2, 7.1)
- CYP3A4 Inducers: Avoid concomitant use of KISQALI FEMARA CO-PACK with strong CYP3A inducers. (7.2)
- CYP3A Substrates: The dose of CYP3A substrates with narrow therapeutic indices may need to be reduced when given concurrently with KISQALI FEMARA CO-PACK. (7.3)
- Drugs Known to Prolong QT Interval: Avoid concomitant use of drugs known to prolong QT interval, such as anti-arrhythmic medicines. (7.4)

8 USE IN SPECIFIC POPULATIONS

Lactation: Advise not to breastfeed. (8.2)

FULL PRESCRIBING INFORMATION

1 INDICATIONS AND USAGE

1.1 Early Breast Cancer

KISQALI® FEMARA® CO-PACK is indicated for the adjuvant treatment of adults with hormone receptor (HR)-positive, human epidermal growth factor receptor 2 (HER2)-negative stage II and III early breast cancer at high risk of recurrence.

1.2 Advanced or Metastatic Breast Cancer

KISQALI® FEMARA® CO-PACK indicated as initial endocrine-based therapy for the treatment of adults with hormone receptor (HR)-positive, human epidermal growth factor receptor 2 (HER2)-negative advanced or metastatic breast cancer.

2 DOSAGE AND ADMINISTRATION

2.1 Recommended Dosage

Important Administration Instructions

The KISQALI FEMARA CO-PACK is comprised of ribociclib tablets co-packaged with letrozole tablets, to provide a 28-day treatment regimen. KISQALI FEMARA CO-PACK can be taken with or without food [see Clinical Pharmacology (12.3)].

Pre/perimenopausal women, or men, treated with KISQALI FEMARA CO-PACK should be treated with a luteinizing hormone-releasing hormone (LHRH) agonist according to current clinical practice standards.

Patients should take their doses of KISQALI FEMARA CO-PACK at approximately the same time each day, preferably in the morning. If the patient vomits after taking the dose or misses a dose, no additional dose should be taken that day. The next prescribed dose should be taken at the usual time. Tablets should be swallowed whole (tablets should not be chewed, crushed or split prior to swallowing). No tablet should be ingested if it is broken, cracked, or otherwise not intact.

Early Breast Cancer

- KISQALI: The recommended dosage of KISQALI is 400 mg (two 200 mg film-coated tablets) taken orally, once daily for 21 consecutive days followed by 7 days off in 28-day treatment cycles.
- FEMARA: 2.5 mg (one tablet) taken once daily throughout the 28-day cycle.

In patients with early breast cancer, treatment with KISQALI should continue for 3 years or until disease recurrence or unacceptable toxicity occurs.

Advanced or Metastatic Breast Cancer

- KISQALI: The recommended dosage for KISQALI is 600 mg (three 200 mg film-coated tablets) taken orally, once daily for 21 consecutive days followed by 7 days off in 28-day treatment cycles.
- FEMARA: 2.5 mg (one tablet) taken once daily throughout the 28-day cycle.

Refer to the Full Prescribing Information for the recommended dosage for each product.

2.2 Dose Modifications

Dose Modifications for Adverse Reactions

The recommended dose modifications of KISQALI for adverse reactions are listed in Table 1.

Dose modifications are not recommended for FEMARA when administered with KISQALI for the adverse reactions of KISQALI, including neutropenia, hepatobiliary toxicity, or QT prolongation [see Dosage and Administration (2)].

Table 1: Recommended Dose Modification of KISQALI FEMARA CO-PACK for Adverse Reactions
Level | KISQALI |  | FEMARA
 | Dose | Number of tablets | Dose | Number of tablets
Early breast cancer
Starting dose | 400 mg/day | two 200 mg tablets | 2.5 mg/day | one 2.5 mg tablet
Dose reduction | 200 mg/day* | one 200 mg tablet | 2.5 mg/day | one 2.5 mg tablet
Advanced or metastatic breast cancer
Starting dose | 600 mg/day | three 200 mg tablets | 2.5 mg/day | one 2.5 mg tablet
First dose reduction | 400 mg/day | two 200 mg tablets | 2.5 mg/day | one 2.5 mg tablet
Second dose reduction | 200 mg/day* | one 200 mg tablet | 2.5 mg/day | one 2.5 mg tablet
*If dose reduction below 200 mg/day is required, discontinue KISQALI.

Tables 2, 3, 4, 5, 6, and 7 summarize recommendations for dose interruption, reduction, or discontinuation of KISQALI in the management of specific adverse reactions. Dose modification of KISQALI FEMARA CO-PACK is recommended based on individual patient safety and tolerability.

Table 2: Dose Modification and Management for Interstitial Lung Disease/Pneumonitis
 | Grade 1 (asymptomatic) | Grade 2 (symptomatic) | Grade 3 (severe symptomatic) or 4 (life-threatening)
ILD/Pneumonitis [see Warnings and Precautions (5.1)] | No dose interruption or adjustment is required. Initiate appropriate medical therapy and monitor as clinically indicated. | Dose interruption until recovery to Grade ≤ 1 then consider resuming KISQALI at the next lower dose level*. If Grade 2 recurs, discontinue KISQALI. | Discontinue KISQALI.
Abbreviation: ILD, interstitial lung disease.
Grading according to Common Terminology Criteria for Adverse Events (CTCAE) version 4.03.
*An individualized benefit-risk assessment should be performed when considering resuming KISQALI.

Table 3: Dose Modification and Management for Cutaneous Adverse Reactions, Including SCARs
 | Grade 1 (< 10% body surface area (BSA) with active skin toxicity, no signs of systemic involvement) | Grade 2 (10%-30% BSA with active skin toxicity, no signs of systemic involvement) | Grade 3 (severe rash not responsive to medical management; > 30% BSA with active skin toxicity, signs of systemic involvement present; SJS*) | Grade 4 (any % BSA associated with extensive superinfection, with IV antibiotics indicated; life threatening consequences; TEN**)
Cutaneous adverse reactions, including SCARs [see Warnings and Precautions (5.2)] | No dose adjustment is required. Initiate appropriate medical therapy and monitor as clinically indicated. |  | Interrupt KISQALI until the etiology of the reaction has been determined. If the etiology is a SCAR, permanently discontinue KISQALI. If the etiology is not a SCAR, interrupt dose until recovery to Grade ≤ 1, then resume KISQALI at same dose level. If the cutaneous adverse reaction still recurs at Grade 3, resume KISQALI at the next lower dose level. | Permanently discontinue KISQALI.
Abbreviations: BSA, body surface area; SCARs, severe cutaneous adverse reactions; SJS, Stevens-Johnson syndrome; TEN, toxic epidermal necrolysis.
*SJS (Grade 3 and 4) is defined as skin sloughing covering < 10% BSA and 10%-30% BSA, respectively, with associated signs (e.g., erythema, purpura, epidermal detachment, and mucous membrane detachment).
**TEN (Grade 4) is defined as skin sloughing covering ≥ 30% BSA with associated symptoms (e.g., erythema, purpura, epidermal detachment, and mucous membrane detachment).
Grading according to Common Terminology Criteria for Adverse Events (CTCAE) version 4.03.

Table 4: Dose Modification and Management of KISQALI for QT Prolongation
QTcF* prolongation | Early breast cancer | Advanced or metastatic breast cancer
> 480 ms and ≤ 500 ms | Interrupt KISQALI treatment and wait until QTcF resolves to ≤ 480 ms
 | Resume at the same dose | Reduce to the next lower dose level
 | If QTcF > 480 ms recurs, interrupt KISQALI treatment and wait until QTcF resolves to ≤ 480 ms, then resume at next lower dose level.
> 500 ms | Interrupt KISQALI treatment and wait until QTcF resolves to ≤ 480 ms, then resume at next lower dose level. If QTcF > 500 ms recurs, discontinue KISQALI.
Permanently discontinue KISQALI if QTcF interval prolongation is either > 500 ms or > 60 ms change from baseline AND associated with any of the following: Torsades de Pointes, polymorphic ventricular tachycardia, syncope, or signs/symptoms of serious arrhythmia.
Note: If dose reduction below 200 mg/day is required, discontinue KISQALI.
Electrocardiograms (ECGs) should be assessed prior to initiation of treatment in all patients.
Repeat ECGs at approximately Day 14 of the first cycle, and as clinically indicated.
In case of QTcF prolongation at any given time during treatment, monitor ECG more frequently, and as clinically indicated.
*QTcF = QT interval corrected by Fridericia’s formula.

Table 5: Dose Modification and Management of KISQALI for Hepatobiliary Toxicity
 | Grade 1 (> ULN – 3 x ULN) | Grade 2 (> 3 to 5 x ULN) | Grade 3 (> 5 to 20 x ULN) | Grade 4 (> 20 x ULN)
AST and/or ALT elevations from baseline*, WITHOUT increase in total bilirubin above 2 x ULN [see Warnings and Precautions (5.4)] | No dose adjustment is required. | Baseline* at < Grade 2: Dose interruption until recovery to ≤ baseline grade, and then resume KISQALI at same dose level. If Grade 2 recurs, resume KISQALI at next lower dose level. ----------------------------- Baseline* at Grade 2: No dose interruption. | Dose interruption until recovery to ≤ baseline* grade, and then resume at next lower dose level. If Grade 3 recurs, discontinue KISQALI. | Discontinue KISQALI.
Combined elevations in AST and/or ALT WITH total bilirubin increase, in the absence of cholestasis [see Warnings and Precautions (5.4)] | If patients develop ALT and/or AST > 3 x ULN along with total bilirubin > 2 x ULN irrespective of baseline grade, discontinue KISQALI.
Perform Liver Function Tests (LFTs) before initiating treatment with KISQALI.
Monitor LFTs every 2 weeks for the first 2 cycles, at the beginning of each subsequent 4 cycles, and as clinically indicated.
If Grade ≥ 2 abnormalities are noted, monitor more frequently, and as clinically indicated.
Abbreviations: AST, aspartate aminotransferase; ALT, alanine aminotransferase; ULN, upper limit of normal.
*Baseline = prior to treatment initiation.
Grading according to Common Terminology Criteria for Adverse Events (CTCAE) version 4.03.

Table 6: Dose Modification and Management of KISQALI for Neutropenia
 | Grade 1 or 2 (ANC 1000/mm^3 – < LLN) | Grade 3 (ANC 500 - < 1000/mm^3) | Grade 3 Febrile* Neutropenia | Grade 4 (ANC < 500/mm^3)
Neutropenia [see Warnings and Precautions (5.5)] | No dose adjustment is required. | Dose interruption until recovery to Grade ≤ 2. Resume KISQALI at the same dose level. If toxicity recurs at Grade 3, dose interruption until recovery, then resume KISQALI at the next lower dose level. | Dose interruption until recovery of neutropenia to Grade ≤ 2. Resume KISQALI at the next lower dose level. | Dose interruption until recovery to Grade ≤ 2. Resume KISQALI at the next lower dose level.
 | Perform complete blood counts (CBCs) before initiating treatment with KISQALI. Monitor CBC every 2 weeks for the first 2 cycles, at the beginning of each subsequent 4 cycles, and as clinically indicated.
Abbreviations: ANC, absolute neutrophil count; LLN, lower limit of normal.
*Grade 3 neutropenia with single episode of fever > 38.3°C (or) 38°C or above for more than one hour and/or concurrent infection.
Grading according to Common Terminology Criteria for Adverse Events (CTCAE) version 4.03.

Table 7: Dose Modification and Management of KISQALI for Other Toxicities*
 | Grade 1 or 2 | Grade 3 | Grade 4
Other toxicities | No dose adjustment is required. Initiate appropriate medical therapy and monitor as clinically indicated. | Dose interruption until recovery to Grade ≤ 1 then resume KISQALI at same dose level. If Grade 3 recurs, resume KISQALI at the next lower dose level. | Discontinue KISQALI.
*Excluding interstitial lung disease (ILD)/pneumonitis, cutaneous adverse reactions, including severe cutaneous adverse reactions (SCARs), QT interval prolongation, hepatobiliary toxicity, and neutropenia.
Grading according to Common Terminology Criteria for Adverse Events (CTCAE) version 4.03.

Refer to the Full Prescribing Information for the coadministered aromatase inhibitor for dose modification guidelines in the event of toxicity and other relevant safety information.

Dose Modification for Use with Strong CYP3A Inhibitors

Avoid concomitant use of KISQALI FEMARA CO-PACK with strong CYP3A inhibitors and consider an alternative concomitant medication with less potential for CYP3A inhibition [see Drug Interactions (7.1)].

If a strong CYP3A inhibitor must be coadministered, reduce the KISQALI dose as shown in Table 8

Table 8: Dose Modification for Use with Strong CYP3A Inhibitors
Indication | Co-administration with Strong CYP3A Inhibitors
Early breast cancer | Reduce the KISQALI dose to 200 mg once daily.
Advanced or metastatic breast cancer | Reduce the KISQALI dose to 400 mg once daily.

If the strong inhibitor is discontinued, change the KISQALI dose (after at least 5 half-lives of the strong CYP3A inhibitor) to the dose used prior to the initiation of the strong CYP3A inhibitor [see Drug Interactions (7.1), Clinical Pharmacology (12.3)].

Dose Modification for Hepatic Impairment

The recommended dose modifications for patients with hepatic impairment are shown in Table 9 [see Use in Specific Populations (8.6), Clinical Pharmacology (12.3)].

Table 9: Dose Modification for Hepatic Impairment
Indication | Mild hepatic impairment (Child-Pugh class A) | Moderate and severe hepatic impairment (Child-Pugh class B or C)
Early breast cancer | No dose adjustment is necessary | No dose adjustment is necessary
Advanced or metastatic breast cancer | No dose adjustment is necessary | KISQALI 400 mg once daily

The dose of FEMARA in patients with cirrhosis and severe hepatic dysfunction should be reduced by 50% [see Clinical Pharmacology (12.3)]. The recommended dose of FEMARA for such patients is 2.5 mg administered every other day. The effect of hepatic impairment on FEMARA exposure in noncirrhotic cancer patients with elevated bilirubin levels has not been determined [see Clinical Pharmacology (12.3)]. Review the Full Prescribing Information for the coadministered aromatase inhibitor or fulvestrant for dose modifications related to hepatic impairment.

Dose Modification for Renal Impairment

The recommended starting dose is 200 mg KISQALI once daily for patients with severe renal impairment [see Use in Specific Populations (8.7), Clinical Pharmacology (12.3)].

No dosage adjustment of FEMARA is required for patients with renal impairment if creatinine clearance is greater than or equal to 10 mL/min [see Clinical Pharmacology (12.3)].

3 DOSAGE FORMS AND STRENGTHS

KISQALI FEMARA CO-PACK is KISQALI (ribociclib) tablets co-packaged with FEMARA (letrozole) tablets.

- Tablet: 200 mg ribociclib (equivalent to 254.40 mg ribociclib succinate).
  Film-coated, light greyish violet, round, curved with beveled edges, debossed with “RIC” on one side and “NVR” on the other side.
- Tablet: 2.5 mg letrozole.
  Dark yellow, film-coated, round, slightly biconvex, with beveled edges (imprinted with the letters “FV” on one side and “CG” on the other side).

4 CONTRAINDICATIONS

Known hypersensitivity to the active substance (letrozole), or to any of the excipients of FEMARA. Refer to FEMARA Prescribing Information.

5 WARNINGS AND PRECAUTIONS

5.1 Interstitial Lung Disease/Pneumonitis

Severe, life-threatening, or fatal interstitial lung disease (ILD) and/or pneumonitis can occur in patients treated with KISQALI and other CDK4/6 inhibitors.

In patients with early breast cancer (NATALEE) who received 400 mg KISQALI plus a non-steroidal aromatase inhibitor (NSAI), 1.5% of patients had ILD/pneumonitis (Grade 1-2).

In patients with advanced or metastatic breast cancer (MONALEESA-2, MONALEESA-7), 1.2% of KISQALI-treated patients had ILD/pneumonitis (any grade, 0.3% had Grade 3-4). Additional cases of ILD/pneumonitis have occurred in the postmarketing setting, some resulting in death [see Adverse Reactions (6.2)].

Monitor patients for pulmonary symptoms indicative of ILD/pneumonitis which may include hypoxia, cough, and dyspnea. In patients who have new or worsening respiratory symptoms suspected to be due to ILD or pneumonitis, interrupt KISQALI immediately and evaluate the patient. Permanently discontinue KISQALI in patients with severe ILD/pneumonitis or any recurrent symptomatic ILD/pneumonitis [see Dosage and Administration (2.2)]. Refer to the Full Prescribing Information for KISQALI®.

5.2 Severe Cutaneous Adverse Reactions

Severe cutaneous adverse reactions (SCARs), including Stevens-Johnson syndrome (SJS), toxic epidermal necrolysis (TEN), and drug-induced hypersensitivity syndrome (DiHS)/drug reaction with eosinophilia and systemic symptoms (DRESS), can occur in patients treated with KISQALI [see Adverse Reactions (6.2)].

If signs or symptoms of SCARs occur, interrupt KISQALI until the etiology of the reaction has been determined [see Dosage and Administration (2.2)]. Early consultation with a dermatologist is recommended to ensure greater diagnostic accuracy and appropriate management.

If SJS, TEN, or DiHS/DRESS is confirmed, permanently discontinue KISQALI. Do not reintroduce KISQALI in patients who have experienced SCARs during KISQALI treatment.

5.3 QT Interval Prolongation

KISQALI has been shown to prolong the QT interval in a concentration-dependent manner [see Clinical Pharmacology (12.2)].

Avoid KISQALI in patients who are at significant risk of developing Torsades de Pointes (TdP), including those with:

- congenital long QT syndrome;
- uncontrolled or significant cardiac disease, recent myocardial infarction, heart failure, unstable angina, bradyarrhythmias, uncontrolled hypertension, high degree atrioventricular block, severe aortic stenosis, or uncontrolled hypothyroidism;
- electrolyte abnormalities;
- taking drugs known to prolong QT interval and/or strong CYP3A inhibitors as this may lead to prolongation of the QTcF interval.

Based on the observed QT prolongation during treatment, KISQALI may require dose interruption, reduction or discontinuation as described in Table 4 [see Dosage and Administration (2.2), Drug Interactions (7.4)].

In patients with early breast cancer (NATALEE) who received 400 mg KISQALI plus NSAI, 8 out of 2494 patients (0.3%) had > 500 ms post-baseline QTcF interval value and 50 out of 2494 patients (2%) had > 60 ms QTcF increase from baseline. QTcF prolongation was reversible with dose interruption. The majority of QTcF prolongation occurred within the first four weeks of KISQALI. There were no reported cases of Torsades de Pointes.

In patients with advanced or metastatic breast cancer (MONALEESA-2 and MONALEESA-7) who received 600 mg KISQALI plus NSAI, 7 out of 574 patients (1%) had a > 500 ms post-baseline QTcF value, and 29 out of 574 patients (5%) had a > 60 ms QTcF increase from baseline. QTcF prolongation was reversible with dose interruption. The majority of QTcF prolongation occurred within the first four weeks of KISQALI. There were no reported cases of Torsades de Pointes.

In MONALEESA-2, in the KISQALI plus letrozole treatment arm, there was one (0.3%) sudden death in a patient with Grade 3 hypokalemia and Grade 2 QT prolongation. No cases of sudden death were reported in MONALEESA-7 [see Adverse Reactions (6)].

Perform ECG in all patients prior to starting KISQALI FEMARA CO-PACK. Initiate treatment with KISQALI FEMARA CO-PACK only in patients with QTcF values less than 450 ms. Repeat ECG at approximately Day 14 of the first cycle, and as clinically indicated.

Monitor serum electrolytes (including potassium, calcium, phosphorous, and magnesium) prior to the initiation of KISQALI FEMARA CO-PACK, at the beginning of the first 6 cycles, and as clinically indicated. Correct any abnormality before starting KISQALI FEMARA CO-PACK [see Dosage and Administration (2.2)].

5.4 Hepatobiliary Toxicity

In patients with early and advanced or metastatic breast cancer, drug-induced liver injury and increases in transaminases occurred with KISQALI.

In patients with early breast cancer (NATALEE) treated with KISQALI, drug-induced liver injury was reported in 9 patients (0.4%), of which 5 were Grade ≥ 3, and 8 had resolved as of the data cutoff. There were 8 (0.3%) clinically confirmed Hy’s Law cases (including 4 out of 9 drug-induced liver injury mentioned above), 6 of which had resolved within 303 days and 2 of which were improving, all after discontinuation of KISQALI. Grade 3 or 4 increases in alanine aminotransferase (ALT) and aspartate aminotransferase (AST) occurred in 8% and 4.7% respectively; including Grade 4 increases in ALT (1.5%) and AST (0.8%).

In patients with advanced or metastatic breast cancer (MONALEESA-2 and MONALEESA-7), treated with KISQALI Grade 3 or 4 increases in ALT and AST occurred in 11% and 8%, respectively.

Among the patients who had Grade ≥ 3 ALT/AST elevation, the median time-to-onset was 111 days for the KISQALI plus aromatase inhibitor treatment arm. The median time to resolution to Grade ≤ 2 was 22 days in the KISQALI plus aromatase inhibitor treatment arm. In MONALEESA-2, concurrent elevations in ALT or AST greater than three times the ULN and total bilirubin greater than two times the ULN, with normal alkaline phosphatase, in the absence of cholestasis (Hy’s Law) occurred in 4 (1%) patients and all patients recovered after discontinuation of KISQALI.

Perform liver function tests (LFTs) in all patients before initiating KISQALI FEMARA CO-PACK. Monitor LFTs every 2 weeks for first 2 cycles, at the beginning of each subsequent 4 cycles, and as clinically indicated [see Dosage and Administration (2.2)].

Based on the severity of the transaminase elevations, KISQALI may require dose interruption, reduction, or discontinuation as described in Table 5 (Dose Modification and Management for Hepatobiliary Toxicity) [see Dosage and Administration (2.2)].

5.5 Neutropenia

KISQALI causes concentration-dependent neutropenia.

In patients with early breast cancer (NATALEE) who received KISQALI plus NSAI, 94%, including 45% of Grade 3 or 4, had a decrease in neutrophil counts (based on laboratory findings), 63% had an adverse reaction of neutropenia, and 0.3% had febrile neutropenia. The median time to Grade ≥ 2 neutropenia was 18 days. The median time to resolution of Grade ≥ 3 neutropenia to Grade < 3 was 10 days. Treatment discontinuation due to neutropenia was required in 1.1% of patients.

In patients with advanced or metastatic breast cancer (MONALEESA-2 and MONALEESA-7), who received KISQALI plus NSAI, 79% had neutropenia, 66% had Grade 3 or 4 decrease in neutrophil count (based on laboratory findings), and 2% had febrile neutropenia. The median time to Grade ≥ 2 neutropenia was 16 days. The median time to resolution of Grade ≥ 3 neutropenia to Grade < 3 was 15 days. Treatment discontinuation due to neutropenia was required in 1% of patients.

Perform a complete blood count (CBC) in all patients before initiating KISQALI FEMARA CO-PACK. Monitor CBC every 2 weeks for the first 2 cycles, at the beginning of each subsequent 4 cycles, and as clinically indicated.

Based on the severity of the neutropenia, KISQALI may require dose interruption, reduction or discontinuation as described in Table 6 [see Dosage and Administration (2.2)].

5.6 Embryo-Fetal Toxicity

Based on findings from animal studies and the mechanism of action, KISQALI FEMARA CO-PACK can cause fetal harm when administered to a pregnant woman. In animal reproduction studies, administration of ribociclib to pregnant rats and rabbits during organogenesis caused embryo-fetal toxicities at maternal exposures that were 0.6 and 1.5 times the human clinical exposure, respectively, based on area under the curve (AUC). Letrozole caused embryo-fetal toxicities in rats and rabbits at maternal exposures that were below the maximum recommended human dose (MRHD) on a mg/m^2 basis.

Advise pregnant women of the potential risk to a fetus. Advise women of reproductive potential to use effective contraception during therapy with KISQALI FEMARA CO-PACK and for at least 3 weeks after the last dose [see Use in Specific Populations (8.1, 8.3), Clinical Pharmacology (12.1)].

6 ADVERSE REACTIONS

The following adverse reactions are discussed in greater detail in other sections of the labeling:

- Interstitial Lung Disease/Pneumonitis [see Warnings and Precautions (5.1)]
- Severe Cutaneous Adverse Reactions [see Warnings and Precautions (5.2)]
- QT Interval Prolongation [see Warnings and Precautions (5.3)]
- Hepatobiliary Toxicity [see Warnings and Precautions (5.4)]
- Neutropenia [see Warnings and Precautions (5.5)]

6.1 Clinical Trials Experience

Because clinical trials are conducted under widely varying conditions, adverse reaction rates observed in the clinical trials of a drug cannot be directly compared to rates in the clinical trials of another drug and may not reflect the rates observed in practice.

The data described in WARNINGS AND PRECAUTIONS reflect exposure to KISQALI plus non-steroidal aromatase inhibitor (NSAI) in 2526 patients with early breast cancer (NATALEE), of whom 51% completed 36 months of KISQALI treatment. The most common (≥ 20%) adverse reactions, including laboratory abnormalities, were lymphocytes decreased (97%), leukocytes decreased (95%), neutrophils decreased (94%), hemoglobin decreased (47%), alanine aminotransferase increased (45%), aspartate aminotransferase increased (44%), infections (37%), creatinine increased (33%), platelets decreased (28%), headache (23%), nausea (23%), and fatigue (22%).

In additions, the pooled safety population described in the WARNINGS AND PRECAUTIONS reflects exposure to KISQALI in 582 patients with advanced or metastatic breast cancer (MONALEESA-2 and MONALEESA-7), of whom 80% were exposed for 6 months or longer and 65% were exposed for greater than one year. The most common (≥ 20%) adverse reactions, including laboratory abnormalities, were leukocytes decreased (94%), neutrophils decreased (94%), hemoglobin decreased (72%), lymphocytes decreased (59%), alanine aminotransferase increased (53%), aspartate aminotransferase increased (53%), infections (46%), nausea (46%), fatigue (36%), platelets decreased (34%), diarrhea (33%), headache (29%), alopecia (29%), vomiting (29%), back pain (25%), constipation (25%), cough (24%), rash (22%), creatinine increased (20%), and abdominal pain (20%).

NATALEE: KISQALI in Combination with a Non-steroidal Aromatase Inhibitor as Adjuvant Treatment

Adults with HR-positive, HER2-negative Stage II and III Early Breast Cancer at High Risk of Recurrence

The safety of KISQALI was evaluated in NATALEE, a clinical trial of 5101 patients who received KISQALI plus NSAI or NSAI alone, with or without goserelin [see Clinical Studies (14)]. The median duration of exposure to KISQALI was 33 months.

Serious adverse reactions occurred in 14% of patients who received KISQALI. Serious adverse reactions in > 0.5% of patients who received KISQALI included COVID-19 (1.1%), pneumonia (0.8%), and pulmonary embolism (0.6%).

Fatal adverse reactions occurred in 0.6% of patients who received KISQALI. Fatal adverse reactions in ≥ 0.1% of patients receiving KISQALI included COVID-19 or COVID-19 pneumonia (0.2%) and pulmonary embolism (0.1%).

Permanent discontinuation of KISQALI due to an adverse reaction occurred in 20% of patients. Adverse reactions which resulted in permanent discontinuation of KISQALI in ≥ 2% of patients were alanine aminotransferase or aspartate aminotransferase increased (8%).

Dosage interruptions of both KISQALI plus NSAI due to an adverse reaction occurred in 73% of patients. Adverse reactions which required dosage interruption in ≥ 5% of patients included neutropenia or neutrophil count decreased (43%), alanine aminotransferase or aspartate aminotransferase increased (11%), COVID-19 (10%), and hypomagnesemia (5%).

Dose reductions of KISQALI due to an adverse reaction occurred in 23% of patients. Adverse reactions which required dose reductions in ≥ 2% of patients included neutropenia or neutrophil count decreased (14%) and liver function abnormal (2.3%).

The most common (≥ 20% on KISQALI plus NSAI and ≥ 2% higher than placebo) adverse reactions, including laboratory abnormalities, were neutropenia, infections, nausea, headache, fatigue, leukopenia, and abnormal liver function tests.

Table 10 summarizes the adverse reactions in NATALEE.

Table 10: Adverse Reactions (≥ 10% and ≥ 2% Higher Than NSAI Alone Arm) in NATALEE
Adverse reaction | KISQALI + NSAI (n = 2526) |  | NSAI (n = 2441)
 | All Grades (%) | Grade 3 or 4 (%) | All Grades (%) | Grade 3 or 4 (%)
Infections and infestations
Infections^1 | 37 | 2.0 | 27 | 0.9
Nervous system disorders
Headache^2 | 23 | 0.4 | 17 | 0.2
Gastrointestinal disorders
Nausea^2 | 23 | 0.2 | 8 | 0.1
Diarrhea^2 | 15 | 0.6 | 6 | 0.1
Constipation^2 | 13 | 0.2 | 5 | 0
Abdominal pain^2 | 11 | 0.5 | 7 | 0.4
General disorders and administration-site conditions
Fatigue^2 | 22 | 0.8 | 13 | 0.2
Asthenia^2 | 17 | 0.6 | 12 | 0.1
Pyrexia^2 | 11 | 0.2 | 6 | 0.1
Skin and subcutaneous tissue disorders
Alopecia | 15 | 0 | 4.6 | 0
Respiratory, thoracic, and mediastinal disorders
Cough^2 | 13 | 0.1 | 8 | 0.1
Grading according to Common Terminology Criteria for Adverse Events (CTCAE) version 4.03.
^1Infections: urinary tract infections; respiratory tract infections.
^2Only includes a Grade 3 adverse reaction.

Clinically relevant adverse reactions reported in < 10% of patients who received KISQALI plus NSAI included rash (9%), dizziness (9%), vomiting (8%), peripheral edema (7%), pruritis (7%), dyspnea (7%), stomatitis (6%), oropharyngeal pain (6%), hypocalcemia (5%), hypokalemia (4.8%), decreased appetite (4.8%).

Table 11 summarizes the laboratory abnormalities in NATALEE.

Table 11: Select Laboratory Abnormalities (≥ 10%) in Patients in NATALEE Who Received KISQALI Plus NSAI
Laboratory abnormality | KISQALI + NSAI (n = 2526) |  | NSAI (n = 2441)
 | All Grades (%) | Grade 3 or 4 (%) | All Grades (%) | Grade 3 or 4 (%)
Hematology
Lymphocytes decreased | 97 | 19 | 88 | 6
Leukocytes decreased | 95 | 27 | 45 | 0.6
Neutrophils decreased | 94 | 45 | 35 | 1.7
Hemoglobin decreased | 47 | 0.6 | 26 | 0.3
Platelets decreased | 28 | 0.4 | 13 | 0.3
Chemistry
Alanine aminotransferase increased | 45 | 8 | 35 | 1
Aspartate aminotransferase increased | 44 | 5 | 33 | 1
Creatinine increased | 33 | 0.3 | 11 | 0

Adverse reactions listed are based on the data of KISQALI in combination with NSAI [anastrozole or letrozole (FEMARA)]. For the complete list of known adverse reactions with KISQALI or FEMARA, see the Full Prescribing Information of KISQALI or FEMARA.

MONALEESA-2: KISQALI in Combination with Letrozole

Postmenopausal Women with HR-positive, HER2-negative Advanced or Metastatic Breast Cancer for Initial Endocrine-Based Therapy

The safety of KISQALI was evaluated in MONALEESA-2, a clinical study of 668 postmenopausal women receiving KISQALI plus letrozole or placebo plus letrozole [see Clinical Studies (14)]. The median duration of exposure to KISQALI plus letrozole was 13 months with 58% of patients exposed for ≥ 12 months.

Serious adverse reactions occurred in 21% of patients who received KISQALI plus letrozole. Serious adverse reactions in ≥1% of patients receiving KISQALI plus letrozole included abdominal pain (1.5%), vomiting (1.5%), constipation (1.2%), nausea (1.2%), anemia (1.2%), febrile neutropenia (1.2%), dyspnea (1.2%), and alanine aminotransferase increased (1.2%).

Fatal adverse reactions occurred in 1.8% of patients who received KISQALI. Fatal adverse reactions in ≥ 0.1% of patients receiving KISQALI included acute respiratory failure (0.6%), acute myocardial infarction, sudden death (with Grade 3 hypokalemia and Grade 2 QT prolongation), unknown cause, and pneumonia (0.3% each). Permanent discontinuation of both KISQALI and letrozole due to an adverse reaction occurred in 7% of patients. Permanent discontinuation of KISQALI alone occurred in 7% of patients. Adverse reactions which resulted in permanent discontinuation of both KISQALI and letrozole in ≥ 2% of patients were alanine aminotransferase increased (5%), aspartate aminotransferase increased (3%), and vomiting (2%).

Dosage interruptions of both KISQALI and letrozole due to an adverse reaction occurred in 71% of patients. Adverse reactions which required dosage interruption in ≥ 5% of patients included neutropenia (39%), neutrophils decreased (12%), vomiting (6%), nausea (5%), alanine aminotransferase increased (5%), and leukocytes decreased (5%).

Dose reductions due to adverse reaction occurred in 45% of patients receiving KISQALI plus letrozole. Adverse reactions which required dose reductions in ≥ 2% of patients included neutropenia (24%), neutrophils decreased (8%), and alanine aminotransferase increased (3%).

Antiemetics and antidiarrheal medications were used to manage symptoms as clinically indicated.

The most common (≥ 20% on the KISQALI arm and ≥ 2% higher than placebo) adverse reactions, including laboratory abnormalities, were neutrophils decreased, leukocytes decreased, hemoglobin decreased, nausea, lymphocytes decreased, alanine aminotransferase increased, aspartate aminotransferase increased, fatigue, diarrhea, alopecia, vomiting, platelets decreased, constipation, headache, and back pain.

Table 12 summarizes the adverse reactions in MONALEESA-2.

Table 12: Adverse Reactions (≥ 10% and ≥ 2% Higher Than Placebo Arm) in MONALEESA-2
Adverse reaction | KISQALI + Letrozole (n = 334) |  | Placebo + Letrozole (n = 330)
 | All Grades (%) | Grade 3 or 4 (%) | All Grades (%) | Grade 3 or 4 (%)
Gastrointestinal disorders
Nausea^1 | 52 | 2.4 | 29 | 0.6
Diarrhea^1 | 35 | 1.2 | 22 | 0.9
Vomiting^1 | 29 | 3.6 | 16 | 0.9
Constipation^1 | 25 | 1.2 | 19 | 0
Stomatitis^1 | 12 | 0.3 | 7 | 0
Abdominal pain^1 | 11 | 1.2 | 8 | 0
General disorders and administration-site conditions
Fatigue | 37 | 2.4 | 30 | 0.9
Pyrexia^1 | 13 | 0.3 | 6 | 0
Edema peripheral^1 | 12 | 0 | 10 | 0
Skin and subcutaneous tissue disorders
Alopecia^1 | 33 | 0 | 16 | 0
Rash^1 | 17 | 0.6 | 8 | 0
Pruritus^1 | 14 | 0.6 | 6 | 0
Nervous system disorders
Headache^1 | 22 | 0.3 | 19 | 0.3
Insomnia^1 | 12 | 0.3 | 9 | 0
Musculoskeletal and connective tissue disorders
Back pain^1 | 20 | 2.1 | 18 | 0.3
Metabolism and nutrition disorders
Decreased appetite^1 | 19 | 1.5 | 15 | 0.3
Respiratory, thoracic and mediastinal disorders
Dyspnea^1 | 12 | 1.2 | 9 | 0.6
Infections and infestations
Urinary tract infections^1 | 11 | 0.6 | 8 | 0
Grading according to Common Terminology Criteria for Adverse Events (CTCAE) version 4.03.
^1Only includes Grade 3 adverse reactions.

Clinically relevant adverse reactions in < 10% of patients in MONALEESA-2 receiving KISQALI plus letrozole included interstitial lung disease (0.3%), lung infiltration (0.3%), pneumonitis (0.3%), and pulmonary fibrosis (0.6%). Table 13 summarizes the laboratory abnormalities in MONALEESA-2.

Table 13: Select Laboratory Abnormalities (≥ 10%) in Patients in MONALEESA-2 Who Received KISQALI Plus Letrozole
Laboratory abnormality | KISQALI + Letrozole (n = 334) |  | Placebo + Letrozole (n = 330)
 | All Grades (%) | Grade 3 or 4 (%) | All Grades (%) | Grade 3 or 4 (%)
Hematology
Leukocytes decreased | 93 | 34 | 29 | 1.5
Neutrophils decreased | 93 | 60 | 24 | 1.2
Hemoglobin decreased | 57 | 1.8 | 26 | 1.2
Lymphocytes decreased | 51 | 14 | 22 | 3.9
Platelets decreased | 29 | 0.9 | 6 | 0.3
Chemistry
Alanine aminotransferase increased | 46 | 10 | 36 | 1.2
Aspartate aminotransferase increased | 44 | 7 | 32 | 1.5
Creatinine increased | 20 | 0.6 | 6 | 0
Phosphorous decreased | 13 | 5 | 4 | 0.6
Potassium decreased | 11 | 1.2 | 7 | 1.2

Adverse reactions listed are based on the data of KISQALI in combination with letrozole (FEMARA). For the complete list of known ARs with KISQALI or FEMARA, see the Full Prescribing Information of KISQALI or FEMARA.

Bone Effects

In MONALEESA-2, with a median duration of safety follow-up of 20.1 months, 12 patients (4%) in the ribociclib plus letrozole arm and 18 patients (6%) in the placebo plus letrozole arm experienced fractures. Osteoporosis (all Grades) was experienced in three patients (0.9%) in the ribociclib plus letrozole arm and 2 patients (0.6%) in the placebo plus letrozole arm.

MONALEESA-7: KISQALI in Combination with an Aromatase Inhibitor

Pre/perimenopausal Patients with HR-positive, HER2-negative Advanced or Metastatic Breast Cancer for Initial Endocrine-Based Therapy

The safety of KISQALI was evaluated in MONALEESA-7, a clinical trial of 672 pre/perimenopausal patients with HR-positive, HER2-negative advanced or metastatic breast cancer receiving either KISQALI plus NSAI or tamoxifen plus goserelin or placebo plus NSAI or tamoxifen plus goserelin [see Clinical Studies (14)]. The median duration of exposure in the KISQALI plus a NSAI arm was 15.2 months with 66% of patients exposed for ≥ 12 months. The safety data reported below are based on 495 pre/perimenopausal patients receiving KISQALI plus NSAI plus goserelin or placebo plus NSAI plus goserelin.

Serious adverse reactions occurred in 17% of patients who received KISQALI plus NSAI plus goserelin. Serious adverse reactions in ≥ 1% of patients receiving KISQALI plus NSAI plus goserelin included drug-induced liver injury (1.6%), abdominal pain (1.2%), dyspnea (1.2%), febrile neutropenia (1.2%), and back pain (1.2%).

Permanent discontinuation of both KISQALI and NSAI due to an adverse reaction occurred in 3% of patients. Permanent discontinuation of KISQALI alone occurred in 3% patients. Adverse reactions which resulted in permanent discontinuation of both KISQALI and NSAI in ≥ 2% of patients were alanine aminotransferase increased (2%), and aspartate aminotransferase increased (2%).

Dosage interruptions of KISQALI plus NSAI plus goserelin due to an adverse reaction occurred in 73% of patients. Adverse reactions which required dosage interruption in ≥ 5% of patients included neutropenia (41%), neutrophils decreased (26%), and leukocytes decreased (6%).

Dose reductions due to an adverse reaction occurred in 33% of patients receiving KISQALI plus NSAI plus goserelin. Adverse reactions which required dose reductions in ≥ 2% of patients included neutropenia (17%), neutrophils decreased (5%), and alanine aminotransferase increased (2%).

The most common (≥ 20% on the KISQALI arm and ≥ 2% higher than placebo) adverse reactions, including laboratory abnormalities, were leukocytes decreased, neutrophils decreased, hemoglobin decreased, lymphocytes decreased, gamma-glutamyl transferase increased, aspartate aminotransferase increased, infections, arthralgia, alanine aminotransferase increased, nausea, platelets decreased, and alopecia.

Table 14 summarizes the adverse reactions in MONALEESA-7.

Table 14: Adverse Reactions (≥ 10% and ≥ 2% Higher Than Placebo Arm) in MONALEESA-7 (NSAI)
Adverse reaction | KISQALI + NSAI + Goserelin (n = 248) |  | Placebo + NSAI + Goserelin (n = 247)
 | All Grades (%) | Grade 3 or 4 (%) | All Grades (%) | Grade 3 or 4 (%)
Infections and infestations
Infections^1,2 | 36 | 1.6 | 24 | 0.4
Musculoskeletal and connective tissue disorders
Arthralgia^2 | 34 | 0.8 | 29 | 1.2
Gastrointestinal disorders
Nausea^2 | 32 | 0 | 20 | 0
Constipation^2 | 16 | 0 | 12 | 0
Stomatitis^2 | 10 | 0 | 8 | 0.4
Skin and subcutaneous tissue disorders
Alopecia^2 | 21 | 0 | 13 | 0
Rash^2 | 17 | 0.4 | 9 | 0
Pruritus^2 | 11 | 0 | 4 | 0
General disorders and administration-site conditions
Pyrexia^2 | 17 | 0.8 | 7 | 0
Pain in extremity^2 | 10 | 0 | 8 | 1.2
Respiratory, thoracic and mediastinal disorders
Cough^2 | 15 | 0 | 10 | 0
Abbreviation: NSAI, non-steroidal aromatase inhibitor.
Grading according to Common Terminology Criteria for Adverse Events (CTCAE) version 4.03.
^1Infections: urinary tract infections; respiratory tract infections; gastroenteritis; sepsis (< 1%).
^2Only includes Grade 3 adverse reactions.

Clinically relevant adverse reactions in < 10% of patients in MONALEESA-7 receiving KISQALI plus NSAI included thrombocytopenia (9%), dry skin (9%), oropharyngeal pain (7%), dyspepsia (5%), lacrimation increased (4%), dry eye (4%), vitiligo (3%), hypocalcemia (2%), blood bilirubin increased (1%), syncope (0.4%), and pneumonitis (0.4%).

Table 15: Select Laboratory Abnormalities (≥ 10%) in Patients in MONALEESA-7 Who Received KISQALI Plus NSAI Plus Goserelin
Laboratory abnormality | KISQALI + NSAI + Goserelin (n = 248) |  | Placebo + NSAI + Goserelin (n = 247)
 | All Grades (%) | Grade 3 or 4 (%) | All Grades (%) | Grade 3 or 4 (%)
Hematology
Leukocytes decreased | 93 | 36 | 30 | 0.8
Neutrophils decreased | 92 | 63 | 27 | 2.4
Hemoglobin decreased | 84 | 2.4 | 51 | 0.4
Lymphocytes decreased | 55 | 14 | 18 | 2.8
Platelets decreased | 26 | 0.4 | 9 | 0.4
Chemistry
Gamma-glutamyl transferase increased | 42 | 7 | 42 | 9
Aspartate aminotransferase increased | 37 | 4.8 | 35 | 1.6
Alanine aminotransferase increased | 33 | 6 | 31 | 1.6
Phosphorous decreased | 14 | 1.6 | 11 | 0.8
Potassium decreased | 11 | 1.2 | 14 | 1.2
Glucose serum decreased | 10 | 0.4 | 10 | 0.4
Creatinine increased | 8 | 0 | 2 | 0

Adverse reactions listed are based on the data of KISQALI in combination with NSAI [anastrozole or letrozole (FEMARA)]. For the complete list of known adverse reactions with KISQALI or FEMARA, see the Full Prescribing Information of KISQALI or FEMARA.

Bone Effects

In MONALEESA-7, with a median duration of safety follow-up of 26.5 months, 4 patients (2%) in the ribociclib plus NSAI subgroup and 7 patients (3%) in the placebo plus NSAI subgroup experienced fractures. No osteoporosis (all Grades) was reported in the ribociclib plus NSAI subgroup, and 1 patient (0.4%) experienced osteoporosis in the placebo plus NSAI subgroup.

COMPLEEMENT-1: KISQALI in Combination with Letrozole and Goserelin or Leuprolide

Men with HR-positive, HER2-negative Advanced Breast Cancer for Initial Endocrine-Based Therapy

The safety of KISQALI in combination with letrozole was evaluated in men (n = 39) in an open-label, multicenter clinical study for the treatment of adult patients with HR-positive, HER2-negative, advanced breast cancer who received no prior hormonal therapy for advanced disease (COMPLEEMENT-1) [see Clinical Studies (14)].

The median duration of exposure to KISQALI was 20.8 months (range, 0.5 to 30.6 months).

Other adverse reactions occurring in men treated with KISQALI plus letrozole and goserelin or leuprolide were similar to those occurring in women treated with KISQALI plus endocrine therapy.

6.2 Postmarketing Experience

The following adverse events have been reported during post-approval use of KISQALI. Because these events are reported voluntarily from a population of uncertain size, it is not always possible to reliably estimate their frequency or establish a causal relationship to drug exposure.

Respiratory disorders: Interstitial lung disease/pneumonitis

Skin and subcutaneous tissue disorders: Stevens-Johnson syndrome (SJS), toxic epidermal necrolysis (TEN), drug-induced hypersensitivity syndrome (DiHS)/drug reaction with eosinophilia, and systemic symptoms (DRESS).

7 DRUG INTERACTIONS

Ribociclib

7.1 Drugs That May Increase Ribociclib Plasma Concentrations

CYP3A4 Inhibitors

Coadministration of a strong CYP3A4 inhibitors increases ribociclib exposure [see Clinical Pharmacology (12.3)]. Increased ribociclib concentrations may increase the incidence and severity of adverse reactions, including QTcF prolongation [see Warnings and Precautions (5.3)]. Avoid concomitant use of strong CYP3A inhibitors with KISQALI and consider alternative concomitant medications with less potential for CYP3A inhibition.

In patients with early breast cancer, if coadministration of KISQALI with a strong CYP3A inhibitor cannot be avoided, reduce the dose of KISQALI to 200 mg once daily. In patients with advanced or metastatic breast cancer, if coadministration of KISQALI with a strong CYP3A inhibitor cannot be avoided, reduce the dose of KISQALI to 400 mg once daily [see Dosage and Administration (2.2)].

7.2 Drugs That May Decrease Ribociclib Plasma Concentrations

CYP3A4 Inducers

Coadministration of a strong CYP3A4 inducers decreases the plasma exposure of ribociclib [see Clinical Pharmacology (12.3)]. Avoid concomitant use of strong CYP3A inducers and consider an alternate concomitant medication with no or minimal potential to induce CYP3A.

7.3 Effect of KISQALI on Other Drugs

CYP3A Substrates

Coadministration of sensitive CYP3A4 substrates with multiple doses of KISQALI increases the substrate exposure [see Clinical Pharmacology (12.3)]. For CYP3A substrates where minimal increases in the concentration may increase CYP3A substrate adverse reactions, monitor for increased adverse reactions of the CYP3A substrate during treatment with KISQALI. The dose of a sensitive CYP3A substrate may need to be reduced as KISQALI can increase its exposure.

7.4 Drugs That Prolong the QT Interval

Avoid coadministration of KISQALI with products with a known potential to prolong QT interval, such as antiarrhythmic drugs that are known to prolong the QT interval. If concomitant use cannot be avoided, monitor ECG when initiating, during concomitant use, and as clinically indicated [see Warnings and Precautions (5.3), Clinical Pharmacology (12.2)].

8 USE IN SPECIFIC POPULATIONS

8.1 Pregnancy

Risk Summary

Based on findings from animal studies and the mechanisms of action, KISQALI FEMARA CO-PACK can cause fetal harm when administered to a pregnant woman [see Clinical Pharmacology (12.1)].

There are no available human data informing the drug-associated risk. In animal reproduction studies, administration of ribociclib to pregnant animals during organogenesis resulted in increased incidences of post implantation loss and reduced fetal weights in rats and increased incidences of fetal abnormalities in rabbits at exposures 0.6 or 1.5 times the exposure in humans, respectively, at the highest recommended dose of 600 mg/day based on AUC (see Data). Advise pregnant women of the potential risk to a fetus.

In animal reproduction studies, administration of letrozole to pregnant animals during organogenesis resulted in increased post-implantation pregnancy loss and resorptions, fewer live fetuses, and fetal malformations affecting the renal and skeletal systems in rats and rabbits at doses approximately 0.1 times the daily MRHD on a mg/m^2 basis (see Data).

The background risk of major birth defects and miscarriage for the indicated population is unknown. However, the background risk of major birth defects is 2% - 4% and of miscarriage is 15% - 20% of clinically recognized pregnancies in the U.S. general population.

Data

Animal Data - Ribociclib

In embryo-fetal development studies in rats and rabbits, pregnant animals received oral doses of ribociclib up to 1000 mg/kg/day and 60 mg/kg/day, respectively, during the period of organogenesis.

In rats, 300 mg/kg/day resulted in reduced maternal body weight gain and reduced fetal weights accompanied by skeletal changes related to the lower fetal weights. There were no significant effects on embryo-fetal viability or fetal morphology at 50 or 300 mg/kg/day.

In rabbits at doses ≥ 30 mg/kg/day, there were adverse effects on embryo-fetal development, including increased incidences of fetal abnormalities (malformations and external, visceral, and skeletal variants) and fetal growth (lower fetal weights). These findings included reduced/small lung lobes, additional vessel on the descending aorta, additional vessel on the aortic arch, small eyes, diaphragmatic hernia, absent accessory lobe or (partly) fused lung lobes, reduced/small accessory lung lobe, extra/rudimentary 13th ribs, misshapen hyoid bone, bent hyoid bone alae and reduced number of phalanges in the pollex. There was no evidence of increased incidence of embryo-fetal mortality. There was no maternal toxicity observed at 30 mg/kg/day.

At 300 mg/kg/day in rats and 30 mg/kg/day in rabbits, the maternal systemic exposures (AUC) were approximately 0.6 and 1.5 times, respectively, the exposure in patients at the highest recommended dose of 600 mg/day.

Animal Data - Letrozole

In a fertility and early embryonic developmental toxicity study in female rats, oral administration of letrozole starting 2 weeks before mating until pregnancy day 6 resulted in an increase in pre-implantation loss at doses ≥ 0.003 mg/kg/day (approximately 0.01 times the MRHD on a mg/m^2 basis).

In an embryo-fetal developmental toxicity study in rats, daily administration of oral letrozole during the period of organogenesis at doses ≥ 0.003 mg/kg (approximately 0.01 times the MRHD on a mg/m^2 basis) resulted in embryo-fetal toxicity, including intrauterine mortality, increased resorptions and postimplantation loss, decreased numbers of live fetuses and fetal anomalies, including absence and shortening of renal papilla, dilation of ureter, edema and incomplete ossification of frontal skull and metatarsals. Letrozole was teratogenic to rats at a dose of 0.03 mg/kg (approximately 0.1 times the MRHD on a mg/m^2 basis) and caused fetal domed head and cervical/centrum vertebral fusion.

In an embryo-fetal developmental toxicity study in rabbits, daily administration of oral letrozole during the period of organogenesis at doses ≥ 0.002 mg/kg (approximately 0.01 the MRHD on a mg/m^2 basis) resulted in embryo-fetal toxicity, including increased resorptions, increased postimplantation loss and decreased numbers of live fetuses. Fetal anomalies included incomplete ossification of the skull, sternebrae, and fore- and hind legs.

8.2 Lactation

Risk Summary

It is not known if ribociclib and letrozole are present in human milk. There are no data on the effects of ribociclib and/or letrozole on the breastfed infant or milk production. Ribociclib and its metabolites readily passed into the milk of lactating rats (see Data). Exposure of lactating rats to letrozole was associated with an impaired reproductive performance of the male offspring (see Data). Because of the potential for serious adverse reactions in breastfed infants from KISQALI FEMARA CO-PACK, advise lactating women not to breastfeed while taking KISQALI FEMARA CO-PACK and for at least 3 weeks after the last dose.

Data

Animal Data - Ribociclib

In lactating rats administered a single dose of 50 mg/kg, exposure to ribociclib was 3.56-fold higher in milk compared to maternal plasma.

Animal Data - Letrozole

In a postnatal developmental toxicity study in lactating rats, letrozole was administered orally at doses of 1, 0.003, 0.03 or 0.3 mg/kg/day on Day 0 through Day 20 of lactation. The reproductive performance of the male offspring was impaired at a letrozole dose as low as 0.003 mg/kg/day (approximately 0.01 the MRHD on a mg/m^2 basis), as reflected by decreased mating and pregnancy ratios. There were no effects on the reproductive performance of female offspring.

8.3 Females and Males of Reproductive Potential

Based on animal studies and mechanisms of action, KISQALI FEMARA CO-PACK can cause fetal harm when administered to a pregnant woman [see Use in Specific Populations (8.1)].

Pregnancy Testing

Verify pregnancy status in females of reproductive potential prior to starting treatment with KISQALI FEMARA CO-PACK.

Contraception

Females

Advise females of reproductive potential to use effective contraception (methods that result in less than 1% pregnancy rates) during treatment with KISQALI FEMARA CO-PACK and for at least 3 weeks after the last dose.

Infertility

Females

Based on studies with letrozole in female animals, KISQALI FEMARA CO-PACK may impair fertility in females of reproductive potential [see Nonclinical Toxicology (13.1)].

Males

Based on animal studies in males, KISQALI FEMARA CO-PACK may impair fertility in males of reproductive potential [see Nonclinical Toxicology (13.1)].

8.4 Pediatric Use

The safety and efficacy of KISQALI FEMARA CO-PACK in pediatric patients have not been established.

Letrozole administration to young (postnatal Day 7) rats for 12 weeks duration at 0.003, 0.03, 0.3 mg/kg/day by oral gavage resulted in adverse skeletal/growth effects (bone maturation, bone mineral density) and neuroendocrine and reproductive developmental perturbations of the hypothalamic-pituitary axis. Administration of 0.3 mg/kg/day resulted in AUC values that were similar to the AUC in adult patients receiving the recommended dose of 2.5 mg/day. Decreased fertility was accompanied by hypertrophy of the hypophysis and testicular changes that included degeneration of the seminiferous tubular epithelium and atrophy of the female reproductive tract. Young rats in this study were allowed to recover following discontinuation of letrozole treatment for 42 days. Histopathological changes were not reversible at clinically relevant exposures.

8.5 Geriatric Use

Of the 2549 adults with early breast cancer who received KISQALI in NATALEE, 407 patients (16%) were ≥ 65 years of age and 123 patients (2.4%) were ≥ 75 years of age. No overall differences in safety or effectiveness of KISQALI were observed between older and younger adults with early breast cancer.

Of 334 patients with advanced or metastatic breast cancer who received KISQALI plus letrozole in MONALEESA-2, 150 patients (45%) were ≥ 65 years of age and 35 patients (11%) were ≥ 75 years of age. No overall differences in safety or effectiveness of KISQALI plus letrozole were observed between older and younger adults with advanced or metastatic breast cancer. Of 248 patients with advanced or metastatic breast cancer who received KISQALI in MONALEESA-7, no patients were ≥ 65 years of age.

8.6 Hepatic Impairment

No dose adjustment of KISQALI is necessary in patients with breast cancer who have mild hepatic impairment (Child-Pugh class A) [see Clinical Pharmacology (12.3)]. A reduced starting dose of 400 mg KISQALI is recommended in patients with advanced or metastatic breast cancer who have moderate (Child-Pugh class B) and severe hepatic impairment (Child-Pugh class C) [see Dosage and Administration (2.2)].

No dose adjustment of FEMARA is necessary in patients with breast cancer who have mild (Child-Pugh class A) to moderate (Child-Pugh class B) hepatic impairment. The dose of FEMARA in patients with cirrhosis and severe hepatic dysfunction should be reduced by 50% [see Clinical Pharmacology (12.3)]. The recommended dose of FEMARA for such patients is 2.5 mg administered every other day. The effect of hepatic impairment on FEMARA exposure in noncirrhotic cancer patients with elevated bilirubin levels has not been determined [see Clinical Pharmacology (12.3)].

8.7 Renal Impairment

No dose adjustment of KISQALI is necessary in patients breast cancer who have mild to moderate (30 mL/min to 89 mL/min/1.73 m^2 ≤ estimated glomerular filtration rate (eGFR)) renal impairment. A reduced starting dose of 200 mg of KISQALI is recommended in patients with breast cancer who have severe renal impairment [see Dosage and Administration (2.2), Clinical Pharmacology (12.3)].

No dosage adjustment of FEMARA is required for patients with renal impairment if creatinine clearance is greater than or equal to 10 mL/min [see Dosage and Administration (2.2), Clinical Pharmacology (12.3)].

11 DESCRIPTION

KISQALI FEMARA CO-PACK consists of ribociclib 200 mg film-coated tablets co-packaged with letrozole 2.5 mg tablets.

Ribociclib

KISQALI (ribociclib) is a kinase inhibitor.

Ribociclib succinate is a light yellow to yellowish brown crystalline powder. The chemical name of ribociclib succinate is: Butanedioic acid—7-cyclopentyl-N,N-dimethyl-2-{[5-(piperazin-1-yl) pyridin-2-yl]amino}-7H-pyrrolo[2,3-d]pyrimidine-6-carboxamide (1/1).

The molecular formula for ribociclib succinate is C23H30N8O.C4H6O4 and the molecular weight is 552.64 g/mol [Free base: 434.55 g/mol].

The chemical structure of ribociclib is shown below:

KISQALI film-coated tablets are supplied for oral use and contain 200 mg of ribociclib free base (equivalent to 254.40 mg ribociclib succinate). The tablets also contain colloidal silicon dioxide, crospovidone, hydroxypropylcellulose, magnesium stearate, and microcrystalline cellulose. The film-coating contains iron oxide black, iron oxide red, lecithin (soya), polyvinyl alcohol (partially hydrolyzed), talc, titanium dioxide, and xanthan gum as inactive ingredients.

Letrozole

FEMARA (letrozole) is a nonsteroidal aromatase inhibitor (inhibitor of estrogen synthesis).

Letrozole is a white to yellowish crystalline powder, practically odorless, freely soluble in dichloromethane, slightly soluble in ethanol, and practically insoluble in water. It has a molecular weight of 285.31 g/mol, empirical formula C17H11N5, and a melting range of 184°C to 185°C.

The chemical name of letrozole is 4,4'-(1H-1,2,4-Triazol-1ylmethylene) dibenzonitrile, and its structural formula is

FEMARA is available as 2.5 mg tablets for oral administration.

Inactive Ingredients: colloidal silicon dioxide, ferric oxide, hydroxypropyl methylcellulose, lactose monohydrate, magnesium stearate, maize starch, microcrystalline cellulose, polyethylene glycol, sodium starch glycolate, talc, and titanium dioxide.

12 CLINICAL PHARMACOLOGY

12.1 Mechanism of Action

Ribociclib is an inhibitor of cyclin-dependent kinase (CDK) 4 and 6. These kinases are activated upon binding to D-cyclins and are downstream of signaling pathways, which lead to cell cycle progression and cellular proliferation. The cyclin D-CDK4/6 complex regulates cell cycle progression through phosphorylation of the retinoblastoma protein (pRb).

In vitro, ribociclib decreased pRb phosphorylation, resulting in arrest in the G1 phase of the cell cycle and reduced cell proliferation in breast cancer-derived lines. In vivo, treatment with single agent ribociclib in a rat xenograft model with human tumor cells led to decreased tumor volumes, which correlated with inhibition of pRb phosphorylation.

Letrozole is a nonsteroidal competitive inhibitor of the aromatase enzyme system by competitively binding to the heme of the cytochrome P450 subunit of the enzyme, resulting in a reduction of estrogen biosynthesis in all tissues. In postmenopausal women, estrogens are mainly derived from the action of the aromatase enzyme, which converts adrenal androgens (primarily androstenedione and testosterone) to estrone and estradiol. The suppression of estrogen biosynthesis in peripheral tissues and in the cancer tissue itself can therefore be achieved by specifically inhibiting the aromatase enzyme.

In studies, using patient-derived estrogen receptor positive breast cancer xenograft models, combination of ribociclib and antiestrogen (e.g., letrozole) therapies resulted in increased tumor growth inhibition compared to each drug alone.

12.2 Pharmacodynamics

The exposure-response relationship and time course of pharmacodynamic response for the safety and effectiveness of KISQALI have not been fully characterized in patients.

Ribociclib

Cardiac Electrophysiology

A concentration-QT analysis of the data in patients with breast cancer treated with KISQALI at doses ranging from 50 to 1200 mg (0.083 to 2 times of the approved recommended high dose) suggested that ribociclib causes concentration-dependent increases in the QTcF interval.

In patients with early breast cancer, the estimated mean QTcF interval change from baseline for the KISQALI 400 mg in combination with non-steroidal aromatase inhibitor (NSAI) was 10.0 ms (90% CI: 8.0, 11.9) at the mean steady-state Cmax [see Warnings and Precautions (5.3, 5.4)].

In patients with advanced or metastatic breast cancer the estimated mean QTcF interval change from baseline for KISQALI 600 mg in combination with aromatase inhibitors was 22.0 ms (90% CI: 22.0, 23.4), and was 34.7 ms (90% CI: 31.6, 37.8) in combination with tamoxifen at the mean Cmax at steady-state [see Warnings and Precautions (5.3)].

Letrozole

In postmenopausal patients with advanced breast cancer, daily doses of 0.1 mg to 5 mg FEMARA (letrozole) suppress plasma concentrations of estradiol, estrone, and estrone sulfate by 75% to 95% from baseline with maximal suppression achieved within two-three days. Suppression is dose-related, with doses of 0.5 mg and higher giving many values of estrone and estrone sulfate that were below the limit of detection in the assays. Estrogen suppression was maintained throughout treatment in all patients treated at 0.5 mg or higher.

Letrozole is highly specific in inhibiting aromatase activity. There is no impairment of adrenal steroidogenesis. No clinically relevant changes were found in the plasma concentrations of cortisol, aldosterone, 11-deoxycortisol, 17-hydroxy-progesterone, adrenocorticotropic hormone (ACTH) or in plasma renin activity among postmenopausal patients treated with a daily dose of FEMARA 0.1 mg to 5 mg. The ACTH stimulation test performed after 6 and 12 weeks of treatment with daily doses of 0.1, 0.25, 0.5, 1, 2.5, and 5 mg did not indicate any attenuation of aldosterone or cortisol production. Glucocorticoid or mineralocorticoid supplementation is, therefore, not necessary.

No changes were noted in plasma concentrations of androgens (androstenedione and testosterone) among healthy postmenopausal women after 0.1, 0.5, and 2.5 mg single doses of FEMARA or in plasma concentrations of androstenedione among postmenopausal patients treated with daily doses of 0.1 mg to 5 mg. This indicates that the blockade of estrogen biosynthesis does not lead to accumulation of androgenic precursors. Plasma levels of luteinizing hormone (LH) and follicle-stimulating hormone (FSH) were not affected by letrozole in patients, nor was thyroid function as evaluated by thyroid stimulating hormone (TSH) levels, T3 uptake, and T4 levels.

12.3 Pharmacokinetics

Ribociclib exhibited over-proportional increases in exposure (Cmax and AUC) across the dose range of 50 mg to 1200 mg (0.083 to 2 times of the approved recommended high dose) following both single dose and repeated doses of KISQALI. Following repeated 600 mg once daily administration, steady-state was generally achieved after 8 days and ribociclib accumulated with a mean accumulation ratio of 2.5 (range, 0.97 to 6.4) and mean (coefficient of variation (CV%)) steady-state ribociclib Cmax was 1820 (62%) ng/mL and AUC was 23800 (66%) ng*h/mL.

Letrozole’s terminal elimination half-life is about 2 days and steady-state plasma concentration after daily 2.5 mg dosing is reached in 2-6 weeks. Plasma concentrations at steady state are 1.5 to 2 times higher than predicted from the concentrations measured after a single dose, indicating a slight non-linearity in the pharmacokinetics of letrozole upon daily administration of 2.5 mg. These steady-state levels are maintained over extended periods, however, and continuous accumulation of letrozole does not occur.

Absorption

Ribociclib

The Tmax following KISQALI administration was between 1 and 4 hours. The mean absolute bioavailability of ribociclib after a single oral dose of 600 mg was 65.8%.

Food Effect: Compared to the fasted state, oral administration of a single 600 mg dose of KISQALI tablet with a high-fat, high-calorie meal (approximately 800 to 1000 calories with ~50% calories from fat, ~35% calories from carbohydrates, and ~15% calories from protein) had no clinically meaningful differences in ribociclib Cmax or AUCinf.

Letrozole

Letrozole is rapidly and completely absorbed from the gastrointestinal tract and absorption is not affected by food. It is metabolized slowly to an inactive metabolite whose glucuronide conjugate is excreted renally, representing the major clearance pathway. About 90% of radiolabeled letrozole is recovered in urine.

Letrozole is weakly protein bound and has a large volume of distribution (approximately 1.9 L/kg).

Metabolism and Elimination/Excretion

Ribociclib

Ribociclib undergoes extensive hepatic metabolism mainly via CYP3A4 in humans. Following oral administration of a single 600 mg dose of radio-labeled ribociclib to humans, the primary metabolic pathways for ribociclib involved oxidation (dealkylation, C and/or N-oxygenation, oxidation (-2H)) and combinations thereof. Ribociclib was the major circulating drug-derived entity in plasma (44%). The major circulating metabolites included metabolite M13 (CCI284, N-hydroxylation), M4 (LEQ803, N-demethylation), and M1 (secondary glucuronide), each representing an estimated 9%, 9%, and 8% of total radioactivity, and 22%, 20%, and 18% of ribociclib exposure. Clinical activity of ribociclib was due primarily to parent drug, with negligible contribution from circulating metabolites.

Ribociclib was extensively metabolized with unchanged drug accounting for 17% and 12% in feces and urine, respectively. Metabolite LEQ803 represented approximately 14% and 4% of the administered dose in feces and urine, respectively.

Elimination

The mean plasma effective half-life (CV%) was 32.0 hours (63%) and the mean apparent oral clearance (CL/F) was 25.5 L/hr (66%) at steady-state following 600 mg dose of KISQALI in patients with advanced cancer. The steady state mean CL/F was 38.4 L/hr following the 400 mg dose of KISQALI in patients with early breast cancer.

The mean apparent plasma terminal half-life of ribociclib ranged from 29.7 to 54.7 hours and mean CL/F of ribociclib ranged from 39.9 to 77.5 L/hr at 600 mg across studies in healthy adults.

Following a single oral dose of radio-labeled ribociclib in healthy adults, 92% of the total administered radioactive dose was recovered within 22 days; 69% in feces and 23% in urine.

Letrozole

Metabolism to a pharmacologically-inactive carbinol metabolite (4,4'methanol-bisbenzonitrile) and renal excretion of the glucuronide conjugate of this metabolite is the major pathway of letrozole clearance. Of the radiolabel recovered in urine, at least 75% was the glucuronide of the carbinol metabolite, about 9% was two unidentified metabolites, and 6% was unchanged letrozole.

In human microsomes with specific CYP isozyme activity, CYP3A4 metabolized letrozole to the carbinol metabolite while CYP2A6 formed both this metabolite and its ketone analog. In human liver microsomes, letrozole inhibited CYP2A6 and inhibited CYP2C19, however, the clinical significance of these findings is unknown.

Specific Populations

Patients with Hepatic Impairment

Ribociclib

Compared to adults with normal hepatic impairment, mild (Child-Pugh class A) hepatic impairment had no effect on the exposure of ribociclib; while in adults with moderate (Child-Pugh class B) hepatic impairment, the mean ratio was 1.44 for Cmax and 1.28 for AUCinf; and with adults with severe (Child-Pugh class C) hepatic impairment, the mean ratio was 1.32 for Cmax and 1.29 for AUCinf.

Letrozole

The effect of hepatic impairment on FEMARA exposure in noncirrhotic cancer patients with elevated bilirubin levels has not been determined.

In a study of subjects with mild to moderate non-metastatic hepatic dysfunction (e.g., cirrhosis, Child-Pugh class A and B), the mean AUC values of the volunteers with moderate hepatic impairment were 37% higher than in normal subjects, but still within the range seen in subjects without impaired function.

In a pharmacokinetic study, subjects with liver cirrhosis and severe hepatic impairment (Child-Pugh class C, which included bilirubins about 2-11 times ULN with minimal to severe ascites) had 2-fold increase in exposure (AUC) and 47% reduction in systemic clearance. Breast cancer patients with severe hepatic impairment are thus expected to be exposed to higher levels of letrozole than patients with normal liver function receiving similar doses of this drug [see Clinical Pharmacology (12.3)].

Patients with Renal Impairment

Ribociclib

In adults with severe renal impairment and end stage renal disease, ribociclib AUCinf increased 2.4-fold and 3.8-fold, and Cmax increased 2.1-fold and 2.7-fold relative to the exposure in adults with normal renal function.

Mild or moderate renal impairment had no effect on the exposure of ribociclib. In a subgroup analysis of data from studies following oral administration of KISQALI in patients with advanced cancer or early breast cancer who have mild to moderate renal impairment, AUC and Cmax were comparable to those in patients with normal renal function, suggesting no clinically meaningful effect of mild or moderate renal impairment on ribociclib exposure.

Letrozole

In a study of volunteers with varying renal function (24-hour creatinine clearance: 9 to 116 mL/min), no effect of renal function on the pharmacokinetics of single doses of 2.5 mg of FEMARA was found. In addition, in a study of 347 patients with advanced breast cancer, about half of whom received 2.5 mg FEMARA and half 0.5 mg FEMARA, renal impairment (calculated creatinine clearance: 20 to 50 mL/min) did not affect steady-state plasma letrozole concentrations.

Effect of Age, Weight, Gender, and Race

No clinically relevant effects of age, body weight, gender, or race on the systemic exposure of ribociclib were identified.

Drug Interaction Studies

Clinical Studies and Model-Informed Approaches

Drugs That Affect Ribociclib Plasma Concentrations

CYP3A Inhibitors: Following a single 400 mg dose of KISQALI with ritonavir (a strong CYP3A inhibitor), ritonavir (100 mg twice a day for 14 days) increased ribociclib Cmax and AUCinf by 1.7-fold and 3.2-fold, respectively, compared to ribociclib alone. Cmax and AUC for LEQ803 (a prominent metabolite of LEE011, accounting for less than 10% of parent exposure) decreased by 96% and 98%, respectively. A moderate CYP3A4 inhibitor (erythromycin) is predicted to increase ribociclib steady-state Cmax and AUC by 1.1-fold and 1.2-fold, respectively, following KISQALI 400 mg once daily, and 1.1-fold and 1.1-fold respectively, following KISQALI 600 mg once daily.

CYP3A Inducers: Following a single 600 mg dose of KISQALI with rifampicin (a strong CYP3A4 inducer) at 600 mg daily for 14 days, ribociclib Cmax decreased by 81% and AUCinf decreased by 89%, while LEQ803 Cmax increased 1.7-fold and AUCinf decreased by 27% compared to ribociclib alone. A moderate CYP3A inducer (efavirenz) is predicted to decrease ribociclib steady-state Cmax by 55% and AUC by 74%, following KISQALI 400 mg once daily, and by 52% and 71% respectively, following KISQALI 600 mg once daily.

Drugs That Are Affected by KISQALI

CYP3A4 and CYP1A2 Substrates: In a cocktail study with midazolam (sensitive CYP3A4 substrate) multiple doses of ribociclib (400 mg once daily for 8 days) increased midazolam Cmax by 2.1-fold and increased AUCinf by 3.8-fold compared to midazolam alone. Administration of KISQALI 600 mg once daily is predicted to increase midazolam Cmax and AUC by 2.4-fold and 5.2-fold, respectively. The effect of multiple doses of 400 mg ribociclib on caffeine (sensitive CYP1A2 substrate) was minimal, with Cmax decreased by 10% and AUCinf increased slightly by 20%. Only weak inhibitory effects on CYP1A2 substrates are predicted at KISQALI 600 mg once daily dose.

Gastric pH-Elevating Agents: Coadministration of ribociclib with drugs that elevate the gastric pH is not predicted to alter ribociclib absorption.

Letrozole: Data from a clinical trial in patients with breast cancer indicated no drug interaction between ribociclib and letrozole following coadministration of the drugs.

Anastrozole: Data from a clinical trial in patients with breast cancer indicated no clinically relevant drug interaction between ribociclib and anastrozole following coadministration of the drugs.

Exemestane: Data from a clinical trial in patients with breast cancer indicated no clinically relevant drug interaction between ribociclib and exemestane following coadministration of the drugs.

Fulvestrant: Data from a clinical trial in patients with breast cancer indicated no clinically relevant effect of fulvestrant on ribociclib exposure following coadministration of the drugs.

Tamoxifen: KISQALI is not indicated for concomitant use with tamoxifen. Data from a clinical trial in patients with breast cancer indicated that tamoxifen Cmax and AUC increased approximately 2-fold following coadministration of KISQALI 600 mg.

In Vitro Studies

Effect of Ribociclib on CYP Enzymes: In vitro, ribociclib was a reversible inhibitor of CYP1A2, CYP2E1, and CYP3A4/5 and a time-dependent inhibitor of CYP3A4/5, at clinically relevant concentrations. In vitro evaluations indicated that ribociclib has no potential to inhibit the activities of CYP2A6, CYP2B6, CYP2C8, CYP2C9, CYP2C19, and CYP2D6 at clinically relevant concentrations. It has no potential for time-dependent inhibition of CYP1A2, CYP2C9, and CYP2D6, and no induction of CYP1A2, CYP2B6, CYP2C9, and CYP3A4 at clinically relevant concentrations.

Effect of Ribociclib on Transporters: In vitro evaluations indicated that ribociclib has a low potential to inhibit the activities of drug transporters P-gp, OATP1B1/B3, OCT1, MATEK2 at clinically relevant concentrations. Ribociclib may inhibit BCRP, OCT2, MATE1, and human BSEP at clinically relevant concentrations.

Effect of Transporters on Ribociclib: Based on in vitro data, P-gp, and BCRP mediated transport are unlikely to affect the extent of oral absorption of ribociclib at therapeutic doses. Ribociclib is not a substrate for hepatic uptake transporters OATP1B1/1B3 or OCT-1 in vitro.

13 NONCLINICAL TOXICOLOGY

13.1 Carcinogenesis, Mutagenesis, Impairment of Fertility

Ribociclib

In a 2-year carcinogenicity study with oral administration of ribociclib daily in cycles of 3 weeks on/1 week off, ribociclib was not carcinogenic at doses up to 50 mg/kg in male rats and 600 mg/kg in female rats. Systemic exposure in male and female rats were 1.3 and 1.8 times, respectively, the human exposure at the highest recommended dose of 600 mg/day based on AUC.

Ribociclib was not mutagenic in an in vitro bacterial reverse mutation (Ames) assay or clastogenic in an in vitro human lymphocyte chromosomal aberration assay or an in vivo rat bone marrow micronucleus assay.

In a fertility and early embryonic development study, female rats received oral doses of ribociclib for 14 days prior to mating through the first week of pregnancy. Ribociclib did not affect reproductive function, fertility or early embryonic development at doses up to 300 mg/kg/day (approximately 0.6 times the clinical exposure in patients at the highest recommended dose of 600 mg/day based on AUC).

A fertility study in male rats has not been performed with ribociclib. In repeat-dose toxicity studies with oral administration of ribociclib daily for 3 weeks on/1 week off in rats up to 26 weeks duration and dogs up to 39 weeks duration, atrophic changes in testes were reported. Findings included degeneration of seminiferous tubular epithelia in the testes and hypospermia and luminal cellular debris in the epididymides of rats and dogs and vacuolation of epithelia in the epididymides of rats. These findings were observed at doses ≥ 75 mg/kg in rats and ≥ 1 mg/kg in dogs which resulted in systemic exposures that were 1.4 and 0.03 times the human exposure at the highest recommended daily dose of 600 mg/day based on AUC, respectively. These effects can be linked to a direct anti-proliferative effect on the testicular germ cells resulting in atrophy of the seminiferous tubules and showed a trend towards reversibility in rats and dogs after a four-week, non-dosing period.

Letrozole

A conventional carcinogenesis study in mice at doses of 0.6 to 60 mg/kg/day (about 1 to 100 times the daily MRHD on a mg/m^2 basis) administered by oral gavage for up to 2 years revealed a dose-related increase in the incidence of benign ovarian stromal tumors. The incidence of combined hepatocellular adenoma and carcinoma showed a significant trend in females when the high dose group was excluded due to low survival. In a separate study, plasma AUC0-12hr levels in mice at 60 mg/kg/day were 55 times higher than the AUC0-24hr level in breast cancer patients at the recommended dose. The carcinogenicity study in rats at oral doses of 0.1 to 10 mg/kg/day (about 0.4 to 40 times the daily MRHD on a mg/m^2 basis) for up to 2 years also produced an increase in the incidence of benign ovarian stromal tumors at 10 mg/kg/day. Ovarian hyperplasia was observed in females at doses equal to or greater than 0.1 mg/kg/day. At 10 mg/kg/day, plasma AUC0-24hr levels in rats were 80 times higher than the level in breast cancer patients at the recommended dose. The benign ovarian stromal tumors observed in mice and rats were considered to be related to the pharmacological inhibition of estrogen synthesis and may be due to increased luteinizing hormone resulting from the decrease in circulating estrogen.

Letrozole was not mutagenic in in vitro tests (Ames and E.coli bacterial tests) but was observed to be a potential clastogen in in vitro assays [Chinese hamster ovary (CHO) K1 and CCL61 CHO cells]. Letrozole was not clastogenic in vivo (micronucleus test in rats).

In a fertility and early embryonic developmental toxicity study in female rats, oral administration of letrozole starting 2 weeks before mating until pregnancy Day 6 resulted in decreases in the incidence of successful mating and pregnancy at doses ≥ 0.03 mg/kg/day (approximately 0.1 times the recommended human dose on a mg/m^2 basis). In repeat-dose toxicity studies, administration of letrozole caused sexual inactivity in females and atrophy of the reproductive tract in males and females at doses of 0.6, 0.1, and 0.03 mg/kg in mice, rats and dogs, respectively (approximately 1, 0.4, and 0.4 times the daily MRHD on a mg/m^2 basis, respectively).

13.2 Animal Toxicology and/or Pharmacology

Ribociclib

In vivo cardiac safety studies in dogs demonstrated dose and concentration related QTc interval prolongation at an exposure similar to patients receiving the recommended dose of 600 mg. There is a potential to induce incidences of premature ventricular contractions (PVCs) at elevated exposures (approximately 5-fold the anticipated clinical Cmax).

14 CLINICAL STUDIES

14.1 Early Breast Cancer

NATALEE: KISQALI in Combination with a Non-steroidal Aromatase Inhibitor (NSAI) with or without Goserelin

Adults with HR-positive, HER2-negative Stage II and III Early Breast Cancer at High Risk of Recurrence

NATALEE (NCT03701334) was a randomized (1:1), open-label, multicenter study in adults (N = 5101) with HR-positive, HER2-negative early breast cancer that was:

- Anatomic Stage Group IIB-III, or
- Anatomic Stage Group IIA that is either:
  - Node positive or
  - Node negative, with:
    - Histologic Grade 3, or
    - Histologic Grade 2, with any of the following criteria:
      - Ki67 ≥ 20%
      - High risk by gene signature testing

Applying TNM criteria, NATALEE included patients with any lymph node involvement, or if no nodal involvement either tumor size > 5 cm, or tumor size 2 to 5 cm with either Grade 2 (and high genomic risk or Ki67 ≥ 20%) or Grade 3.

Participants were randomized to receive KISQALI 400 mg plus a non-steroidal aromatase inhibitor (NSAI, letrozole or anastrozole) or NSAI only, and goserelin as indicated. Randomization was stratified by Anatomic Stage, prior treatment (neoadjuvant versus adjuvant chemotherapy), menopausal status (premenopausal and males versus postmenopausal) and region (North America/Western Europe/Oceania versus rest of the world).

The main efficacy outcome measure was invasive disease-free survival (iDFS). iDFS was defined as the time from randomization to the first occurrence of: local invasive breast recurrence, regional invasive recurrence, distant recurrence, death (any cause), contralateral invasive breast cancer, or second primary non-breast invasive cancer (excluding basal and squamous cell carcinomas of the skin). Overall survival (OS) was an additional outcome measure.

KISQALI was given orally at a dose of 400 mg once daily for 21 consecutive days followed by 7 days off treatment in combination with letrozole 2.5 mg or anastrozole 1 mg orally once daily for 28 days; goserelin 3.6 mg was administered on Day 1 of each 28-day cycle. KISQALI was administered for up to 36 months in the absence of recurrence or unacceptable toxicity. NSAI was administered for at least 5 years.

The median age was 52 years (range, 24 to 90); > 99% women (n = 19 men); 73% White, 13% Asian, 1.7% Black or African American, < 0.1% Native Hawaiian or other Pacific Islander, < 0.1% American Indian or Alaskan Native; 8.5% Hispanic or Latino; 99% ECOG 0-1; 88% node positive disease; 88% received prior (neo)adjuvant chemotherapy.

A statistically significant improvement in iDFS was observed in the intent-to-treat (ITT) population at an interim analysis. The efficacy results at the time of the final iDFS analysis are summarized in Table 16 and Figure 1. At the time of the iDFS final analysis, OS was immature, and a total of 172 (3.5%) of patients had died across both study arms.

Table 16: Efficacy Results – NATALEE (Investigator Assessment, Intent-to-Treat Population)
 | KISQALI + NSAI +/- Goserelin | NSAI +/- Goserelin
Invasive Disease-Free Survival (iDFS)a | N = 2549 | N = 2552
Events (n, %) | 226 (8.9%) | 283 (11.1%)
Hazard ratio (95% CI) | 0.749 (0.628 to 0.892)
iDFS at 36 months (%, 95% CI) | 90.7 (89.3, 91.8) | 87.6 (86.1, 88.9)
Abbreviations: CI, confidence interval; iDFS, invasive disease-free survival.
aiDFS was statistically significant at an interim analysis based on a one-sided stratified log-rank p-value of 0.0014.

Figure 1: Kaplan-Meier Plot of iDFS – NATALEE (Investigator Assessment, Intent-to-Treat Population)

14.2 Advanced or Metastatic Breast Cancer

MONALEESA-2: KISQALI in Combination with Letrozole

Postmenopausal Women with HR-positive, HER2-negative Advanced or Metastatic Breast Cancer for Initial Endocrine-Based Therapy

MONALEESA-2 (NCT01958021) was a randomized (1:1), double-blind, placebo-controlled, multicenter clinical study of KISQALI plus letrozole vs. placebo plus letrozole conducted in postmenopausal women (N = 668) with HR-positive, HER2-negative, advanced breast cancer who received no prior therapy for advanced disease.

Participants were randomized to receive either KISQALI and letrozole or placebo and letrozole, stratified according to the presence of liver and/or lung metastases. Letrozole 2.5 mg was given orally once daily for 28 days, with either KISQALI 600 mg or placebo orally once daily for 21 consecutive days followed by 7 days off until disease progression or unacceptable toxicity. The major efficacy outcome measure for the study was investigator-assessed progression-free survival (PFS) using Response Evaluation Criteria in Solid Tumors (RECIST v1.1).

The median age of 62 years (range, 23 to 91) and 45% of patients were older than 65. The majority of patients were White (82%), and all patients had an ECOG performance status of 0 or 1. A total of 47% of patients had received chemotherapy and 51% had received anti-hormonal therapy in the neoadjuvant or adjuvant setting. Thirty-four percent (34%) of patients had de novo metastatic disease, 21% had bone-only disease, and 59% had visceral disease.

The efficacy results are summarized in Table 17, Figure 2, and Figure 3. The PFS assessment based on a blinded independent central radiological review was consistent with investigator assessment.

Consistent results were observed across patient subgroups of prior adjuvant or neoadjuvant chemotherapy or hormonal therapies, liver and/or lung involvement, and bone-only metastatic disease.

Table 17: Efficacy Results – MONALEESA-2 (Investigator Assessment, Intent-to-Treat Population)
 | KISQALI + Letrozole | Placebo + Letrozole
Progression-Free Survival | N = 334 | N = 334
Events (n, %) | 93 (27.8) | 150 (44.9)
Median (months, 95% CI) | NR (19.3 – NR) | 14.7 (13.0 – 16.5)
Hazard ratio (95% CI) | 0.556 (0.429, 0.720)
p-valuea | < 0.0001a
Overall Survival | N = 334 | N = 334
Events (n, %) | 181 (54.2) | 219 (65.6)
Median (months, 95% CI) | 63.9 (52.4, 71.0) | 51.4 (47.2, 59.7)
Hazard ratio (95% CI) | 0.765 (0.628, 0.932)
p-value | 0.004a
Overall Response Rate for patients with measurable disease | N = 256 | N = 245
Overall Response Rate (95% CI) | 52.7 (46.6, 58.9) | 37.1 (31.1, 43.2)
Abbreviations: CI, confidence interval; NR, not reached.
ap-value estimated from one-sided log-rank test.

Figure 2 Kaplan-Meier Plot of Progression-Free Survival – MONALEESA-2 (Investigator Assessment, Intent-to-Treat Population)

Figure 3 Kaplan-Meier plot of Overall Survival Curves – MONALEESA-2 (Intent-to-Treat Population)

MONALEESA-7: KISQALI in Combination with a Non-Steroidal Aromatase Inhibitor with or without Goserelin

Pre/perimenopausal Patients with HR-positive, HER2-negative Advanced or Metastatic Breast Cancer for Initial Endocrine-Based Therapy

MONALEESA-7 (NCT02278120) was a randomized (1:1), double-blind, placebo-controlled study of KISQALI plus either NSAI or tamoxifen and goserelin vs. placebo plus either a NSAI or tamoxifen and goserelin conducted in pre/perimenopausal women (N = 672) with HR-positive, HER2-negative, advanced breast cancer who received no prior endocrine therapy for advanced disease.

Participants were randomized to receive KISQALI plus NSAI or tamoxifen plus goserelin or placebo plus NSAI or tamoxifen plus goserelin, stratified according to the presence of liver and/or lung metastases, prior chemotherapy for advanced disease, and endocrine combination partner (tamoxifen and goserelin vs. NSAI and goserelin).

NSAI (letrozole 2.5 mg or anastrozole 1 mg) or tamoxifen 20 mg were given orally once daily on a continuous daily schedule, goserelin was administered as a sub-cutaneous injection on Day 1 of each 28-day cycle, with either KISQALI 600 mg or placebo orally once daily for 21 consecutive days followed by 7 days off until disease progression or unacceptable toxicity. The major efficacy outcome measure for the study was investigator-assessed progression-free survival (PFS) using Response Evaluation Criteria in Solid Tumors (RECIST) v1.1.

The median age was 44 years (range, 25 to 58). Patients were primarily White (58%), Asian (29%), or Black (3%). Nearly all patients (99%) had an ECOG performance status of 0 or 1. Of the 672 patients, 33% had received chemotherapy in the adjuvant vs. 18% in the neoadjuvant setting and 40% had received endocrine therapy in the adjuvant vs. 0.7% in the neoadjuvant setting prior to study entry. Forty percent (40%) of patients had de novo metastatic disease, 24% had bone-only disease, and 57% had visceral disease. Demographics and baseline disease characteristics were balanced and comparable between study arms, and endocrine combination partner.

The efficacy results from a pre-specified subgroup analysis of 495 patients who had received KISQALI or placebo with NSAI plus goserelin are summarized in Table 18, Figure 4, and Figure 5. Consistent results were observed in the stratification factor subgroups of disease site and prior chemotherapy for advanced disease.

Table 18: Efficacy Results – MONALEESA-7 (NSAI, Investigator Assessment)
 | KISQALI + NSAI + Goserelin | Placebo + NSAI + Goserelin
Progression-Free Survival^1 | N = 248 | N = 247
Events (n, %) | 92 (37.1) | 132 (53.4)
Median (months, 95% CI) | 27.5 (19.1, NR) | 13.8 (12.6, 17.4)
Hazard ratio (95% CI) | 0.569 (0.436, 0.743)
Overall Survival | N = 248 | N = 247
Events (n, %) | 61 (24.6) | 80 (32.4)
Median (months, 95% CI) | NR (NR, NR) | 40.7 (37.4, NR)
Hazard ratio (95% CI) | 0.699 (0.501, 0.976)
Overall Response Rate for patients with measurable disease*,1 | N = 192 | N = 199
Overall Response Rate (95% CI) | 50.5 (43.4, 57.6) | 36.2 (29.5, 42.9)
Abbreviations: CI, confidence interval; NR, not reached; NSAI, non-steroidal aromatase inhibitors.
*Based on confirmed responses.
^1Investigator Assessment.

Figure 4 Kaplan-Meier Plot of Progression-Free Survival Curves – MONALEESA-7 (NSAI, Investigator Assessment)

Figure 5 Kaplan-Meier Plot of Overall Survival - MONALEESA-7 (NSAI, Investigator Assessment)

COMPLEEMENT-1: KISQALI in combination with Letrozole and Goserelin or Leuprolide

Men with HR-positive, HER2-negative Advanced or Metastatic Breast Cancer for Initial Endocrine-Based Therapy

COMPLEEMENT-1 (NCT 02941926) was an open-label, multicenter clinical study of ribociclib in combination with letrozole and goserelin or leuprolide for the treatment of adults with HR-positive, HER2-negative, advanced breast cancer who received no prior hormonal therapy for advanced disease.

The study included 39 male patients who received KISQALI 600 mg orally once daily for 21 consecutive days followed by 7 days off; and letrozole 2.5 mg orally once daily for 28 days; and goserelin 3.6 mg as injectable subcutaneous implant or leuprolide 7.5 mg as intramuscular injection administered on Day 1 of each 28-day cycle. Patients were treated until disease progression or unacceptable toxicity occurred.

Male patients enrolled in this study had a median age of 62 years (range, 33 to 80). Of these patients, 39% were 65 years and older, including 10% aged 75 years and older. The male patients enrolled were White (72%), Asian (8%), and Black (3%), with 17% unknown. Nearly all male patients (97%) had an ECOG performance status of 0 or 1. The majority of male patients (97%) had 4 or less metastatic sites, which were primarily bone and visceral (69% each). Table 19 summarizes the efficacy results in male patients from COMPLEEMENT-1.

Table 19: Efficacy Results in Male Patients^1 – COMPLEEMENT-1 (Investigator Assessment, Intent-to-Treat Population)
 | KISQALI + Letrozole + Goserelin or Leuprolide
Overall Response Rate for patients with measurable disease*,2 | N = 32
Overall Response Rate (95% CI) | 46.9 (29.1, 65.3)
Duration of Response (DoR)^3 | N = 15
Median (months, 95% CI) | NR (21.3, NR)
Patients with DoR ≥12 months, n (%) | 12 (80.0)
Abbreviations: CI, confidence interval, NR, not reached.
*Based on confirmed responses.
^1Patients with measurable disease.
^2Investigator Assessment.
^3Patients with complete response or partial response.

16 HOW SUPPLIED/STORAGE AND HANDLING

KISQALI FEMARA CO-PACK is dispensed in a carton for a total of 28 days of therapy.

Each carton contains individual ribociclib and letrozole drug products as follows:

KISQALI (ribociclib) Tablets:

200 mg tablets.

Light greyish violet, round, curved with beveled edge, debossed with “RIC” on one side and “NVR” on the other side.

FEMARA (letrozole) Tablets:

2.5 mg tablets.

Dark yellow, round, slightly biconvex, with beveled edges, imprinted with the letters “FV” on one side and “CG” on the other side.

KISQALI FEMARA CO-PACK Cartons:

- NDC 0078-0923-61 – Carton of 3 blister packs (63 tablets total) – each blister pack contains a 7-day supply of 21 tablets (200 mg per tablet) (600 mg daily dose) of KISQALI plus one 28-tablet count bottle of FEMARA
- NDC 0078-0916-61 – Carton of 3 blister packs (42 tablets total) – each blister pack contains a 7-day supply of 14 tablets (200 mg per tablet) (400 mg daily dose) of KISQALI plus one 28-tablet count bottle of FEMARA
- NDC 0078-0909-61 – Carton of 1 blister pack (21 tablets total) – each blister pack contains a 21-day supply of 21 tablets (200 mg per tablet) (200 mg daily dose) of KISQALI plus one 28-tablet count bottle of FEMARA

Store at room temperature at 20°C to 25°C (68°F to 77°F), excursions permitted between 15°C and 30°C (59°F and 86°F).

Store in the original blister package in order to protect from moisture.

17 PATIENT COUNSELING INFORMATION

Advise the patient to read the FDA-approved patient labeling (Patient Information).

For additional information on KISQALI and FEMARA, refer to the full prescribing information for each product.

Interstitial Lung Disease/Pneumonitis

Advise patients to immediately report new or worsening respiratory symptoms [see Warnings and Precautions (5.1)].

Severe Cutaneous Adverse Reactions

Inform patients of the signs and symptoms of severe cutaneous adverse reactions (e.g., skin pain/burning, rapidly-spreading skin rash, and/or mucosal lesions accompanied by fever or flu-like symptoms). Advise patients to contact their healthcare provider immediately if they develop signs and symptoms of severe cutaneous adverse reactions [see Warnings and Precautions (5.2)].

QT Prolongation

Inform patients of the signs and symptoms of QT prolongation. Advise patients to contact their healthcare provider immediately for signs or symptoms of QT prolongation [see Warnings and Precautions (5.3)].

Hepatobiliary Toxicity

Inform patients of the signs and symptoms of hepatobiliary toxicity. Advise patients to contact their healthcare provider immediately for signs or symptoms of hepatobiliary toxicity [see Warnings and Precautions (5.4)].

Neutropenia

Advise patients of the possibility of developing neutropenia and to immediately contact their healthcare provider should they develop a fever, particularly in association with any suggestion of infection [see Warnings and Precautions (5.5)].

Embryo-Fetal Toxicity

- Advise pregnant women and females of reproductive potential of the potential risk to a fetus. Advise females to inform their healthcare provider of a known or suspected pregnancy.
- Advise females of reproductive potential to use effective contraception during KISQALI FEMARA CO-PACK therapy and for at least 3 weeks after the last dose. [see Warnings and Precautions (5.6), Use in Specific Populations (8.1, 8.3)].

Lactation

Advise lactating women not to breastfeed during treatment with KISQALI FEMARA CO-PACK and for at least 3 weeks after the last dose [see Use in Specific Populations (8.2)].

Drug Interactions

- Inform patients to avoid strong CYP3A inhibitors, strong CYP3A inducers, and drugs known to prolong the QT interval [see Drug Interactions (7.1, 7.2, 7.4)].

Infertility

Inform males of reproductive potential that KISQALI may impair fertility [see Use in Specific Populations (8.3)].

Dosing

- Instruct patients to take the doses of KISQALI FEMARA CO-PACK at approximately the same time every day and to swallow tablets whole (do not chew, crush, or split them prior to swallowing) [see Dosage and Administration (2.1)].
- If patient vomits or misses a dose, advise the patient to take the next prescribed dose at the usual time [see Dosage and Administration (2.1)].
- Advise the patient that KISQALI FEMARA CO-PACK may be taken with or without food [see Dosage and Administration (2.1)].

Distributed by:
Novartis Pharmaceuticals Corporation
East Hanover, New Jersey 07936

© Novartis

T2025-59

PATIENT INFORMATION
KISQALI® FEMARA® CO-PACK (kis kah' lee fe ma' ra koe' pak)
(ribociclib tablets; letrozole tablets)
co-packaged for oral use

What is the most important information I should know about KISQALI FEMARA CO-PACK?
KISQALI FEMARA CO-PACK may cause serious side effects, including:

- Lung problems. KISQALI may cause severe or life-threatening inflammation of the lungs during treatment that may lead to death. Tell your healthcare provider right away if you have any new or worsening symptoms, including:
  - trouble breathing or shortness of breath
  - cough with or without mucus
  - chest pain
- Severe skin reactions. Tell your healthcare provider or get medical help right away if you get severe rash or rash that keeps getting worse, reddened skin, flu-like symptoms, skin pain or burning, blistering of the lips, eyes or mouth, blisters on the skin or skin peeling, with or without fever.
- Heart rhythm problems (QT prolongation). KISQALI FEMARA CO-PACK can cause a heart problem known as QT prolongation. This condition can cause an abnormal heartbeat and may lead to death.
  - Your healthcare provider should check your heart and do blood tests before and during treatment with KISQALI FEMARA CO-PACK.
  - Tell your healthcare provider right away if you have a change in your heartbeat (a fast or irregular heartbeat), or if you feel dizzy or faint.
- Liver problems. KISQALI FEMARA CO-PACK can cause serious liver problems. Your healthcare provider will do blood tests to check your liver before and during treatment with KISQALI FEMARA CO-PACK. Tell your healthcare provider right away if you get any of the following signs and symptoms of liver problems:

o yellowing of your skin or the whites of your eyes (jaundice)
o dark or brown (tea-colored) urine
o feeling very tired

o loss of appetite
o pain on the upper right side of your stomach area (abdomen)
o bleeding or bruising more easily than normal

- Low white blood cell counts (neutropenia). Low white blood cell counts are very common during treatment with KISQALI FEMARA CO-PACK and may result in infections that may be severe. Your healthcare provider should check your white blood cell counts before and during treatment with KISQALI FEMARA CO-PACK. Tell your healthcare provider right away if you have signs and symptoms of low white blood cell counts or infections, such as fever and chills.

Your healthcare provider may tell you to decrease your dose, temporarily stop or completely stop taking KISQALI if you develop certain serious side effects during treatment with KISQALI.
See “What are the possible side effects of KISQALI FEMARA CO-PACK?” for more information about side effects.

What is KISQALI FEMARA CO-PACK?
KISQALI FEMARA CO-PACK is a prescription medicine used to treat adults with hormone receptor (HR)-positive, human epidermal growth factor receptor 2 (HER2)-negative breast cancer:

- in combination with aromatase inhibitor for stage II and III early breast cancer with a high risk of coming back.
- That has gotten worse or has spread to other parts of the body (advanced or metastatic breast cancer) in combination with an aromatase inhibitor as the first endocrine-based therapy.
  KISQALI FEMARA CO-PACK contains 2 different types of medicines:
  - The violet tablet contains the medicine KISQALI (ribociclib).
  - The yellow tablet contains the medicine FEMARA (letrozole).
  It is not known if KISQALI FEMARA CO-PACK is safe and effective in children.

Do not take KISQALI FEMARA CO-PACK if you are allergic to letrozole or any of the ingredients of FEMARA.

See the end of this Patient Information for a list of the ingredients in KISQALI FEMARA CO-PACK.

Before taking KISQALI FEMARA CO-PACK, tell your healthcare provider about all your medical conditions, including if you:

- have any heart problems, including heart failure, irregular heartbeats, and QT prolongation
- have ever had a heart attack
- have a slow heartbeat (bradycardia)
- have high blood pressure that is not controlled
- have decreased thyroid gland function (hypothyroidism)
- have problems with the amount of potassium, calcium, phosphorus, or magnesium in your blood
- have fever, chills, or any other signs or symptoms of infection
- have liver problems
- have kidney problems
- are pregnant, or plan to become pregnant. KISQALI FEMARA CO-PACK can harm your unborn baby.
  - If you are able to become pregnant, your healthcare provider should do a pregnancy test before you start treatment with KISQALI FEMARA CO-PACK.
  - Females who are able to become pregnant and who take KISQALI FEMARA CO-PACK should use effective birth control during treatment and for at least 3 weeks after the last dose of KISQALI FEMARA CO-PACK.
  - Talk to your healthcare provider about birth control methods that may be right for you during this time.
  - If you become pregnant or think you are pregnant, tell your healthcare provider right away.
- are breastfeeding or plan to breastfeed. It is not known if KISQALI FEMARA CO-PACK passes into your breast milk. Do not breastfeed during treatment with KISQALI FEMARA CO-PACK and for at least 3 weeks after the last dose of KISQALI FEMARA CO-PACK.

Tell your healthcare provider about all the medicines you take, including prescription and over-the-counter medicines, vitamins, and herbal supplements. KISQALI FEMARA CO-PACK and other medicines may affect each other causing side effects. Know the medicines you take. Keep a list of them to show your healthcare provider or pharmacist when you get a new medicine.

How should I take KISQALI FEMARA CO-PACK?

- Take KISQALI FEMARA CO-PACK exactly as your healthcare provider tells you.
- Do not change your dose or stop taking KISQALI FEMARA CO-PACK without talking to your healthcare provider.
- KISQALI FEMARA CO-PACK comes in a carton that contains enough KISQALI tablets and FEMARA tablets for 28 days of treatment.
- Take KISQALI FEMARA CO-PACK each day at about the same time, preferably in the morning.
- Take KISQALI FEMARA CO-PACK with food or without food.
- Swallow KISQALI tablets and FEMARA tablets whole. Do not chew, crush or split tablets before swallowing them.
- Do not take any KISQALI tablets and FEMARA tablets that are broken, cracked, or that look damaged.
- If you miss a dose or vomit after taking a dose of KISQALI FEMARA CO-PACK, do not take another dose on that day. Take your next dose at your regular time.

What are the possible side effects of KISQALI FEMARA CO-PACK?
KISQALI FEMARA CO-PACK may cause serious side effects.

- See "What is the most important information I should know about KISQALI FEMARA CO-PACK?"

The most common side effects of KISQALI in people with early breast cancer include:

• decreased white blood cell counts
• decreased red blood cell counts
• increased liver function tests
• infections
• increased kidney function test

• decreased platelet counts
• nausea
• headache
• tiredness

The most common side effects of KISQALI FEMARA CO-PACK in people with advanced or metastatic breast cancer include:

• decreased white blood cell counts
• decreased red blood cell counts
• increased liver function tests

• infections
• nausea
• tiredness
• decreased platelet counts
• diarrhea

• headache
• hair loss
• vomiting
• back pain
• constipation
• cough

• rash
• increased kidney function test
• stomach-area (abdomen) pain

KISQALI FEMARA CO-PACK may cause fertility problems in females and males, which may affect your ability to have children. Talk to your healthcare provider if this is a problem for you.
These are not all of the possible side effects of KISQALI FEMARA CO-PACK.
Call your doctor for medical advice about side effects. You may report side effects to FDA at 1-800-FDA-1088.

How should I store KISQALI FEMARA CO-PACK?

- Store KISQALI FEMARA CO-PACK at room temperature between 68°F to 77°F (20°C to 25°C).
- Store KISQALI FEMARA CO-PACK in the original blister package in order to protect from moisture.

Keep KISQALI FEMARA CO-PACK and all medicines out of the reach of children.

General information about the safe and effective use of KISQALI FEMARA CO-PACK.

Medicines are sometimes prescribed for purposes other than those listed in a Patient Information leaflet. Do not use KISQALI FEMARA CO-PACK for a condition for which it was not prescribed. Do not give KISQALI FEMARA CO-PACK to other people, even if they have the same symptoms you have. It may harm them. You can ask your healthcare provider or pharmacist for more information about KISQALI FEMARA CO-PACK that is written for health professionals.

What are the ingredients in KISQALI FEMARA CO-PACK?

KISQALI (ribociclib) tablets:

Active ingredient: ribociclib

Inactive ingredients: colloidal silicon dioxide, crospovidone, hydroxypropylcellulose, magnesium stearate and microcrystalline cellulose. The film-coating contains iron oxide black, iron oxide red, lecithin (soya), polyvinyl alcohol (partially hydrolyzed), talc, titanium dioxide, and xanthan gum

FEMARA (letrozole) tablets:

Active ingredient: letrozole

Inactive ingredients: colloidal silicon dioxide, ferric oxide, hydroxypropyl methylcellulose, lactose monohydrate, magnesium stearate, maize starch, microcrystalline cellulose, polyethylene glycol, sodium starch glycolate, talc, and titanium dioxide

Distributed by: Novartis Pharmaceuticals Corporation, East Hanover, New Jersey 07936

© Novartis

For more information, go to www.KISQALI.com or call 1-888-669-6682.

This Patient Information has been approved by the U.S. Food and Drug Administration.

Revised: September 2025

T2025-60

PRINCIPAL DISPLAY PANEL

NDC 0078-0909-61

Rx only

28-Day supply

Kisqali® Femara® CO-PACK
(ribociclib tablets; letrozole tablets)

200 mg daily dose

(one 200 mg tablet)

21 Film-coated tablets

2.5 mg per tablet

28 Film-coated tablets

NOVARTIS

PRINCIPAL DISPLAY PANEL

NDC 0078-0916-61

Rx only

28-Day supply

Kisqali® Femara® CO-PACK
(ribociclib tablets; letrozole tablets)

400 mg daily dose

(two 200 mg tablets)

42 Film-coated tablets

2.5 mg per tablet

28 Film-coated tablets

NOVARTIS

PRINCIPAL DISPLAY PANEL

NDC 0078-0923-61

Rx only

28-Day supply

Kisqali® Femara® CO-PACK
(ribociclib tablets; letrozole tablets)

600 mg daily dose

(three 200 mg tablets)

63 Film-coated tablets

2.5 mg per tablet

28 Film-coated tablets

NOVARTIS